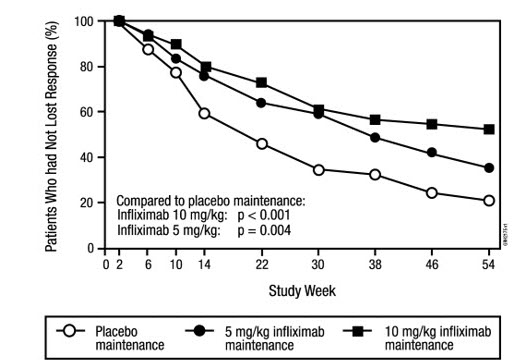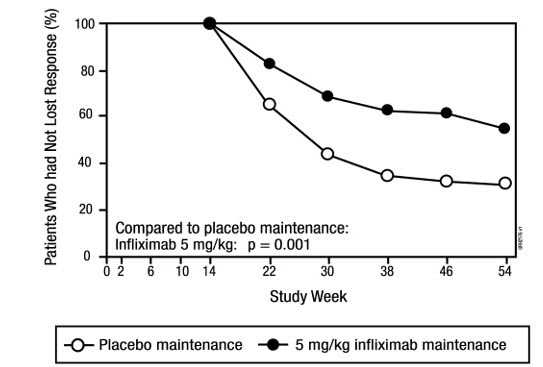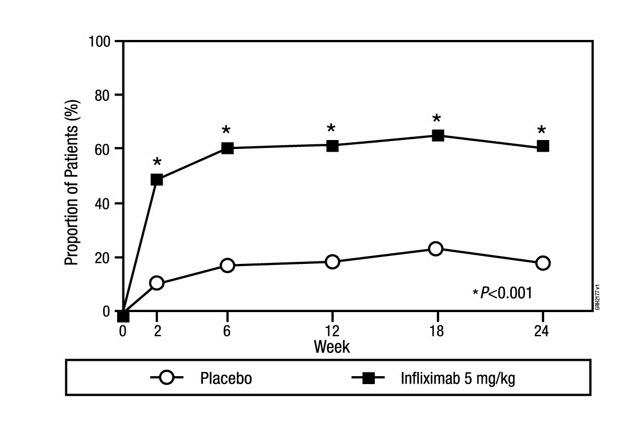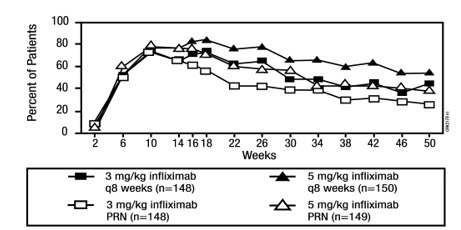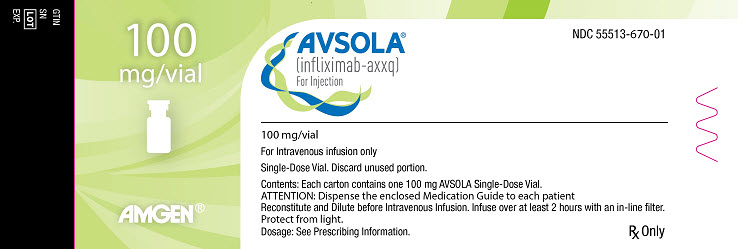 DRUG LABEL: AVSOLA
NDC: 55513-670 | Form: INJECTION, POWDER, LYOPHILIZED, FOR SOLUTION
Manufacturer: Amgen, Inc
Category: prescription | Type: HUMAN PRESCRIPTION DRUG LABEL
Date: 20250908

ACTIVE INGREDIENTS: INFLIXIMAB 100 mg/10 mL
INACTIVE INGREDIENTS: SODIUM PHOSPHATE, DIBASIC, ANHYDROUS 4.9 mg/10 mL; SODIUM PHOSPHATE, MONOBASIC, MONOHYDRATE 2.2 mg/10 mL; POLYSORBATE 80 0.5 mg/10 mL; SUCROSE 500 mg/10 mL

HIGHLIGHTS OF PRESCRIBING INFORMATION

These highlights do not include all the information needed to use AVSOLA®safely and effectively. See full prescribing information for AVSOLA.
AVSOLA (infliximab-axxq) for injection, for intravenous use
Initial U.S. Approval: 2019
AVSOLA (infliximab-axxq) is biosimilar [Biosimilar means that the biological product is approved based on data demonstrating that it is highly similar to an FDA-approved biological product, known as a reference product, and that there are no clinically meaningful differences between the biosimilar product and the reference product. Biosimilarity of AVSOLA has been demonstrated for the condition(s) of use (e.g., indication(s), dosing regimen(s)), strength(s), dosage form(s), and route(s) of administration described in its Full Prescribing Information.] to REMICADE (infliximab).

WARNING: SERIOUS INFECTIONS and MALIGNANCY

See full prescribing information for complete boxed warning.

- Increased risk of serious infections leading to hospitalization or death, including tuberculosis (TB), bacterial sepsis, invasive fungal infections (such as histoplasmosis) and infections due to other opportunistic pathogens. (5.1)
- Discontinue AVSOLA if a patient develops a serious infection.
- Perform test for latent TB; if positive, start treatment for TB prior to starting AVSOLA. Monitor all patients for active TB during treatment, even if initial latent TB test is negative. (5.1)
- Lymphoma and other malignancies, some fatal, have been reported in children and adolescent patients treated with tumor necrosis factor (TNF) blockers, including infliximab products. (5.2)
- Postmarketing cases of fatal hepatosplenic T-cell lymphoma (HSTCL) have been reported in patients treated with TNF blockers including infliximab products. Almost all had received azathioprine or 6-mercaptopurine concomitantly with a TNF blocker at or prior to diagnosis. The majority of cases were reported in patients with Crohn's disease or ulcerative colitis, most of whom were adolescent or young adult males. (5.2)

1 INDICATIONS AND USAGE

AVSOLA is a tumor necrosis factor (TNF) blocker indicated for:

- Crohn's Disease:
  - reducing signs and symptoms and inducing and maintaining clinical remission in adult patients with moderately to severely active disease who have had an inadequate response to conventional therapy. (1.1)
  - reducing the number of draining enterocutaneous and rectovaginal fistulas and maintaining fistula closure in adult patients with fistulizing disease. (1.1)
- Pediatric Crohn's Disease: reducing signs and symptoms and inducing and maintaining clinical remission in pediatric patients 6 years of age and older with moderately to severely active disease who have had an inadequate response to conventional therapy. (1.2)
- Ulcerative Colitis: reducing signs and symptoms, inducing and maintaining clinical remission and mucosal healing, and eliminating corticosteroid use in adult patients with moderately to severely active disease who have had an inadequate response to conventional therapy. (1.3)
- Pediatric Ulcerative Colitis: reducing signs and symptoms and inducing and maintaining clinical remission in pediatric patients 6 years of age and older with moderately to severely active disease who have had an inadequate response to conventional therapy. (1.4)
- Rheumatoid Arthritis in combination with methotrexate: reducing signs and symptoms, inhibiting the progression of structural damage, and improving physical function in adult patients with moderately to severely active disease. (1.5)
- Ankylosing Spondylitis: reducing signs and symptoms in adult patients with active disease. (1.6)
- Psoriatic Arthritis: reducing signs and symptoms of active arthritis, inhibiting the progression of structural damage, and improving physical function in adult patients. (1.7)
- Plaque Psoriasis: treatment of adult patients with chronic severe (i.e., extensive and/or disabling) plaque psoriasis who are candidates for systemic therapy and when other systemic therapies are medically less appropriate. (1.8)

2 DOSAGE AND ADMINISTRATION

- Prior to treatment, ensure appropriate personnel and medication are available to treat reactions (e.g., hypersensitivity) that occur during infusion and shortly after infusion. (2.11)
- AVSOLA is administered by intravenous infusion for at least 2 hours with an in-line filter. (2.11)
- Crohn's Disease: 5 mg/kg at 0, 2 and 6 weeks, then every 8 weeks. Some adult patients who initially respond to treatment may benefit from increasing the dose to 10 mg/kg every 8 weeks if they later lose their response. (2.1)
- Pediatric Crohn's Disease (≥6 years old): 5 mg/kg at 0, 2 and 6 weeks, then every 8 weeks. (2.2)
- Ulcerative Colitis: 5 mg/kg at 0, 2 and 6 weeks, then every 8 weeks. (2.3)
- Pediatric Ulcerative Colitis (≥6 years old): 5 mg/kg at 0, 2 and 6 weeks, then every 8 weeks. (2.4)
- Rheumatoid Arthritis: In conjunction with methotrexate, 3 mg/kg at 0, 2 and 6 weeks, then every 8 weeks. Some patients may benefit from increasing the dose up to 10 mg/kg every 8 weeks or treating as often as every 4 weeks. (2.5)
- Ankylosing Spondylitis: 5 mg/kg at 0, 2 and 6 weeks, then every 6 weeks. (2.6)
- Psoriatic Arthritis and Plaque Psoriasis: 5 mg/kg at 0, 2 and 6 weeks, then every 8 weeks. (2.7, 2.8)

3 DOSAGE FORMS AND STRENGTHS

For injection: 100 mg of infliximab-axxq as a lyophilized powder in a single-dose vial for reconstitution and dilution. (2.11, 3)

4 CONTRAINDICATIONS

- AVSOLA doses >5 mg/kg in moderate or severe heart failure. (4)
- Previous severe hypersensitivity reaction to infliximab products or any inactive ingredients of AVSOLA or to any murine proteins. (4)

5 WARNINGS AND PRECAUTIONS

- Serious infections – do not give AVSOLA during an active infection. If an infection develops, monitor carefully and stop AVSOLA if infection becomes serious. (5.1)
- Invasive fungal infections – for patients who develop a systemic illness on AVSOLA, consider empiric antifungal therapy for those who reside or travel to regions where mycoses are endemic. (5.1)
- Malignancies – the incidence of malignancies, including invasive cervical cancer and lymphoma, was greater in infliximab-treated patients than in controls. Due to the risk of HSTCL carefully assess the risk/benefit especially if the patient has Crohn's disease or ulcerative colitis, is male, and is receiving azathioprine or 6-mercaptopurine treatment. (5.2)
- Hepatitis B virus reactivation – test for HBV infection before starting AVSOLA. Monitor HBV carriers during and several months after therapy. If reactivation occurs, stop AVSOLA and begin anti-viral therapy. (5.3)
- Hepatotoxicity – severe hepatic reactions, some fatal or necessitating liver transplantation. Stop AVSOLA in cases of jaundice and/or marked liver enzyme elevations. (5.4)
- Heart failure – new onset or worsening symptoms may occur. (4, 5.5)
- Cytopenias – advise patients to seek immediate medical attention if signs and symptoms develop, and consider stopping AVSOLA. (5.6)
- Hypersensitivity – serious infusion reactions including anaphylaxis or serum sickness-like reactions may occur. (5.7)
- Cardiovascular and Cerebrovascular Reactions – Cerebrovascular accidents, myocardial infarctions (some fatal), and arrhythmias have been reported during and within 24 hours of initiation of infliximab product infusion. Monitor patients during AVSOLA infusion and if serious reaction occurs, discontinue infusion. (5.8)
- Demyelinating disease – exacerbation or new onset may occur. (5.9)
- Lupus-like syndrome – stop AVSOLA if syndrome develops. (5.12)
- Vaccinations and Use of Live Vaccines/Therapeutic Infectious Agents – Prior to initiating AVSOLA bring pediatric and adult patients up to date with all vaccinations. Live vaccines or therapeutic infectious agents should not be given with AVSOLA. At least a six-month waiting period following birth is recommended before the administration of live vaccines to infants exposed in utero to infliximab products. (5.13)

6 ADVERSE REACTIONS

Most common adverse reactions (>10%) – infections (e.g., upper respiratory, sinusitis, and pharyngitis), infusion-related reactions, headache, and abdominal pain. (6.1)

To report SUSPECTED ADVERSE REACTIONS, contact Amgen Medical Information at 1-800-77-AMGEN (1-800-772-6436) or FDA at 1-800-FDA-1088 or www.fda.gov/medwatch.

7 DRUG INTERACTIONS

Other Biological Products – increased risk of serious infections. (7.1)

FULL PRESCRIBING INFORMATION

WARNING: SERIOUS INFECTIONS and MALIGNANCY

SERIOUS INFECTIONS

Patients treated with infliximab products are at increased risk for developing serious infections that may lead to hospitalization or death [see Warnings and Precautions (5.1) and Adverse Reactions (6.1)]. Most patients who developed these infections were taking concomitant immunosuppressants such as methotrexate or corticosteroids.

AVSOLA should be discontinued if a patient develops a serious infection or sepsis.

Reported infections include:

- Active tuberculosis, including reactivation of latent tuberculosis. Patients with tuberculosis have frequently presented with disseminated or extrapulmonary disease. Patients should be tested for latent tuberculosis before AVSOLA use and during therapy. Treatment for latent infection should be initiated prior to AVSOLA use.
- Invasive fungal infections, including histoplasmosis, coccidioidomycosis, candidiasis, aspergillosis, blastomycosis, and pneumocystosis. Patients with histoplasmosis or other invasive fungal infections may present with disseminated, rather than localized, disease. Antigen and antibody testing for histoplasmosis may be negative in some patients with active infection. Empiric anti-fungal therapy should be considered in patients at risk for invasive fungal infections who develop severe systemic illness.
- Bacterial, viral and other infections due to opportunistic pathogens, including Legionella and Listeria.

The risks and benefits of treatment with AVSOLA should be carefully considered prior to initiating therapy in patients with chronic or recurrent infection.

Patients should be closely monitored for the development of signs and symptoms of infection during and after treatment with AVSOLA, including the possible development of tuberculosis in patients who tested negative for latent tuberculosis infection prior to initiating therapy.

MALIGNANCY

Lymphoma and other malignancies, some fatal, have been reported in children and adolescent patients treated with TNF blockers, including infliximab products [see Warnings and Precautions (5.2)].

Postmarketing cases of hepatosplenic T-cell lymphoma (HSTCL), a rare type of T-cell lymphoma, have been reported in patients treated with TNF blockers including infliximab products. These cases have had a very aggressive disease course and have been fatal. Almost all patients had received treatment with azathioprine or 6-mercaptopurine concomitantly with a TNF blocker at or prior to diagnosis. The majority of reported cases have occurred in patients with Crohn's disease or ulcerative colitis and most were in adolescent and young adult males.

1 INDICATIONS AND USAGE

1.1 Crohn's Disease

AVSOLA is indicated for:

- reducing signs and symptoms and inducing and maintaining clinical remission in adult patients with moderately to severely active Crohn's disease (CD) who have had an inadequate response to conventional therapy.
- reducing the number of draining enterocutaneous and rectovaginal fistulas and maintaining fistula closure in adult patients with fistulizing CD.

1.2 Pediatric Crohn's Disease

AVSOLA is indicated for reducing signs and symptoms and inducing and maintaining clinical remission in pediatric patients 6 years of age and older with moderately to severely active CD who have had an inadequate response to conventional therapy.

1.3 Ulcerative Colitis

AVSOLA is indicated for reducing signs and symptoms, inducing and maintaining clinical remission and mucosal healing, and eliminating corticosteroid use in adult patients with moderately to severely active ulcerative colitis (UC) who have had an inadequate response to conventional therapy.

1.4 Pediatric Ulcerative Colitis

AVSOLA is indicated for reducing signs and symptoms and inducing and maintaining clinical remission in pediatric patients 6 years of age and older with moderately to severely active UC who have had an inadequate response to conventional therapy.

1.5 Rheumatoid Arthritis

AVSOLA, in combination with methotrexate, is indicated for reducing signs and symptoms, inhibiting the progression of structural damage, and improving physical function in adult patients with moderately to severely active rheumatoid arthritis (RA).

1.6 Ankylosing Spondylitis

AVSOLA is indicated for reducing signs and symptoms in adult patients with active ankylosing spondylitis (AS).

1.7 Psoriatic Arthritis

AVSOLA is indicated for reducing signs and symptoms of active arthritis, inhibiting the progression of structural damage, and improving physical function in adult patients with psoriatic arthritis (PsA).

1.8 Plaque Psoriasis

AVSOLA is indicated for the treatment of adult patients with chronic severe (i.e., extensive and/or disabling) plaque psoriasis (Ps) who are candidates for systemic therapy and when other systemic therapies are medically less appropriate. AVSOLA should only be administered to patients who will be closely monitored and have regular follow-up visits with a physician [see Boxed Warning and Warnings and Precautions (5)].

2 DOSAGE AND ADMINISTRATION

2.1 Dosage in Adult Crohn's Disease

The recommended dosage of AVSOLA is 5 mg/kg given as an intravenous induction regimen at 0, 2 and 6 weeks followed by a maintenance regimen of 5 mg/kg every 8 weeks thereafter for the treatment of adults with moderately to severely active CD or fistulizing CD. For adult patients who respond and then lose their response, consideration may be given to treatment with 10 mg/kg every 8 weeks. Patients who do not respond by Week 14 are unlikely to respond with continued dosing and consideration should be given to discontinue AVSOLA in these patients.

2.2 Dosage in Pediatric Crohn's Disease

The recommended dosage of AVSOLA for pediatric patients 6 years and older with moderately to severely active CD is 5 mg/kg given as an intravenous induction regimen at 0, 2 and 6 weeks followed by a maintenance regimen of 5 mg/kg every 8 weeks.

2.3 Dosage in Adult Ulcerative Colitis

The recommended dosage of AVSOLA is 5 mg/kg given as an intravenous induction regimen at 0, 2 and 6 weeks followed by a maintenance regimen of 5 mg/kg every 8 weeks thereafter for the treatment of adult patients with moderately to severely active UC.

2.4 Dosage in Pediatric Ulcerative Colitis

The recommended dosage of AVSOLA for pediatric patients 6 years and older with moderately to severely active UC is 5 mg/kg given as an intravenous induction regimen at 0, 2 and 6 weeks followed by a maintenance regimen of 5 mg/kg every 8 weeks.

2.5 Dosage in Rheumatoid Arthritis

The recommended dosage of AVSOLA is 3 mg/kg given as an intravenous induction regimen at 0, 2 and 6 weeks followed by a maintenance regimen of 3 mg/kg every 8 weeks thereafter for the treatment of moderately to severely active RA. AVSOLA should be given in combination with methotrexate. For patients who have an incomplete response, consideration may be given to adjusting the dosage up to 10 mg/kg every 8 weeks or treating as often as every 4 weeks bearing in mind that risk of serious infections is increased at higher doses per infusion or more frequent dosing [see Adverse Reactions (6.1)].

2.6 Dosage in Ankylosing Spondylitis

The recommended dosage of AVSOLA is 5 mg/kg given as an intravenous induction regimen at 0, 2 and 6 weeks followed by a maintenance regimen of 5 mg/kg every 6 weeks thereafter for the treatment of active AS.

2.7 Dosage in Psoriatic Arthritis

The recommended dosage of AVSOLA is 5 mg/kg given as an intravenous induction regimen at 0, 2 and 6 weeks followed by a maintenance regimen of 5 mg/kg every 8 weeks thereafter for the treatment of PsA. AVSOLA can be used with or without methotrexate.

2.8 Dosage in Plaque Psoriasis

The recommended dosage of AVSOLA in adult patients is 5 mg/kg given as an intravenous induction regimen at 0, 2 and 6 weeks followed by a maintenance regimen of 5 mg/kg every 8 weeks thereafter for the treatment of chronic severe (i.e., extensive and/or disabling) Ps.

2.9 Assessment for Latent and Active Tuberculosis

Prior to initiating AVSOLA and periodically during therapy, patients should be evaluated for active tuberculosis and tested for latent infection [see Warnings and Precautions (5.1)].

2.10 Administration Instructions Regarding Infusion Reactions

Prior to treatment, ensure appropriate personnel and medication are available to treat reactions (e.g., hypersensitivity, other reactions) that occur during infusion and shortly after infusion. Prior to infusion with AVSOLA, patients may be premedicated with histamine-1 receptor antagonists, histamine-2 receptor antagonists, acetaminophen, and/or corticosteroids [see Warnings and Precautions (5.7)].

For mild to moderate reactions during the infusion, consider slowing or stopping the infusion. Upon resolution of these reactions, may reinitiate at a lower infusion rate and/or with histamine-1 receptor antagonists, histamine-2 receptor antagonists, acetaminophen, and/or corticosteroids. Discontinue the infusion if the mild to moderate reactions reoccur.

Discontinue the infusion if severe hypersensitivity reactions occur during the infusion.

2.11 Reconstitution, Dilution, and Administration Instructions

AVSOLA is intended for use under the guidance and supervision of a healthcare provider. The supplied lyophilized powder must be reconstituted and diluted prior to administration. The infusion solution should be prepared and administered by a trained medical professional using aseptic technique by the following procedure:

1. Calculate the dose, total volume of reconstituted AVSOLA solution required and the number of AVSOLA vials needed. More than one vial may be needed for a full dose.
2. Reconstitute each 100 mg AVSOLA vial with 10 mL of Sterile Water for Injection, USP, to obtain a concentration of 10 mg/mL, using a syringe equipped with a 21-gauge or smaller needle as follows:
  - Remove the flip-top from the vial and wipe the top with an alcohol swab.
  - Insert the syringe needle into the vial through the center of the rubber stopper and direct the stream of Sterile Water for Injection, USP, to the glass wall of the vial. Gently swirl the solution by rotating the vial to dissolve the lyophilized powder, which has a cake-like appearance. Avoid prolonged or vigorous agitation. DO NOT SHAKE. Foaming of the solution on reconstitution is not unusual.
  - Allow the reconstituted solution to stand for 5 minutes. Visually inspect the reconstituted solution for particulate matter and discoloration. The reconstituted solution should be colorless to light yellow and opalescent, and the solution may develop a few translucent particles as infliximab-axxq is a protein. Do not use if the lyophilized powder has not fully dissolved or if opaque particles, discoloration, or other foreign particles are present. Do not store unused reconstituted AVSOLA solution.
3. Dilute the total volume of the reconstituted AVSOLA solution to 250 mL [For volumes greater than 250 mL, either use a larger infusion bag (e.g. 500 mL) or multiple 250 mL infusion bags to ensure that the concentration of the infusion solution does not exceed 4 mg/mL.] with sterile 0.9% Sodium Chloride Injection, USP, (do not dilute with any other diluent) as follows:
  - Withdraw a volume from the 0.9% Sodium Chloride Injection, USP, 250 mL bottle or bag equal to the total volume of reconstituted AVSOLA required for a dose. Slowly add the total volume of reconstituted AVSOLA solution from the vial(s) to the 250 mL infusion bottle or bag.
  - Discard any unused portion of the reconstituted AVSOLA solution remaining in the vial(s).
  - Gently invert the bag to mix the solution. The resulting infusion concentration should range between 0.4 mg/mL (minimum recommended concentration) and 4 mg/mL (maximum recommended concentration) of infliximab-axxq.
4. The AVSOLA infusion should begin within 3 hours of reconstitution and dilution. The infusion must be administered intravenously for at least 2 hours with an infusion set with an in-line, sterile, non-pyrogenic, low-protein-binding filter (pore size of 1.2 µm or less).
5. Given that the vials do not contain antibacterial preservatives, discard any unused portion of the infusion solution (do not store for reuse).

No physical biochemical compatibility studies have been conducted to evaluate the co-administration of AVSOLA with other agents. AVSOLA should not be infused concomitantly in the same intravenous line with other agents.

3 DOSAGE FORMS AND STRENGTHS

For injection: 100 mg of infliximab-axxq as a white to slightly yellow lyophilized powder in a single-dose vial for reconstitution and dilution.

4 CONTRAINDICATIONS

The use of AVSOLA at doses >5 mg/kg is contraindicated in patients with moderate or severe heart failure [see Warnings and Precautions (5.5) and Adverse Reactions (6.1)].

AVSOLA is contraindicated in patients with a previous severe hypersensitivity reaction to infliximab products or any of the inactive ingredients of AVSOLA or any murine proteins [severe hypersensitivity reactions have included anaphylaxis, hypotension, and serum sickness] [see Warnings and Precautions (5.7) and Adverse Reactions (6.1)].

5 WARNINGS AND PRECAUTIONS

5.1 Serious Infections

Patients treated with infliximab products are at increased risk for developing serious infections involving various organ systems and sites that may lead to hospitalization or death.

Opportunistic infections due to bacterial, mycobacterial, invasive fungal, viral, or parasitic organisms including aspergillosis, blastomycosis, candidiasis, coccidioidomycosis, cryptococcosis, histoplasmosis, legionellosis, listeriosis, pneumocystosis, salmonellosis and tuberculosis have been reported with TNF blockers. Patients have frequently presented with disseminated rather than localized disease.

Treatment with AVSOLA should not be initiated in patients with an active infection, including clinically important localized infections. Patients greater than 65 years of age, patients with co-morbid conditions and/or patients taking concomitant immunosuppressants such as corticosteroids or methotrexate may be at greater risk of infection. The risks and benefits of treatment should be considered prior to initiating therapy in patients:

- with chronic or recurrent infection;
- who have been exposed to tuberculosis;
- with a history of an opportunistic infection;
- who have resided or traveled in areas of endemic tuberculosis or endemic mycoses, such as histoplasmosis, coccidioidomycosis, or blastomycosis; or
- with underlying conditions that may predispose them to infection.

Tuberculosis

Cases of reactivation of tuberculosis or new tuberculosis infections have been observed in patients receiving infliximab products, including patients who have previously received treatment for latent or active tuberculosis. Cases of active tuberculosis have also occurred in patients being treated with infliximab products during treatment for latent tuberculosis.

Patients should be evaluated for tuberculosis risk factors and tested for latent infection prior to initiating AVSOLA and periodically during therapy. Treatment of latent tuberculosis infection prior to therapy with TNF blockers has been shown to reduce the risk of tuberculosis reactivation during therapy. Induration of 5 mm or greater with tuberculin skin testing should be considered a positive test result when assessing if treatment for latent tuberculosis is needed prior to initiating AVSOLA, even for patients previously vaccinated with Bacille Calmette-Guérin (BCG).

Anti-tuberculosis therapy should also be considered prior to initiation of AVSOLA in patients with a past history of latent or active tuberculosis in whom an adequate course of treatment cannot be confirmed, and for patients with a negative test for latent tuberculosis but having risk factors for tuberculosis infection. Consultation with a physician with expertise in the treatment of tuberculosis is recommended to aid in the decision whether initiating anti-tuberculosis therapy is appropriate for an individual patient.

Tuberculosis should be strongly considered in patients who develop a new infection during AVSOLA treatment, especially in patients who have previously or recently traveled to countries with a high prevalence of tuberculosis, or who have had close contact with a person with active tuberculosis.

Monitoring

Patients should be closely monitored for the development of signs and symptoms of infection during and after treatment with AVSOLA, including the development of tuberculosis in patients who tested negative for latent tuberculosis infection prior to initiating therapy. Tests for latent tuberculosis infection may also be falsely negative while on therapy with AVSOLA.

AVSOLA should be discontinued if a patient develops a serious infection or sepsis. A patient who develops a new infection during treatment with AVSOLA should be closely monitored, undergo a prompt and complete diagnostic workup appropriate for an immunocompromised patient, and appropriate antimicrobial therapy should be initiated.

Invasive Fungal Infections

For patients who reside or travel in regions where mycoses are endemic, invasive fungal infection should be suspected if they develop a serious systemic illness. Appropriate empiric antifungal therapy should be considered while a diagnostic workup is being performed. Antigen and antibody testing for histoplasmosis may be negative in some patients with active infection. When feasible, the decision to administer empiric antifungal therapy in these patients should be made in consultation with a physician with expertise in the diagnosis and treatment of invasive fungal infections and should take into account both the risk for severe fungal infection and the risks of antifungal therapy.

5.2 Malignancies

Malignancies, some fatal, have been reported among children, adolescents and young adults who received treatment with TNF blockers (initiation of therapy ≤18 years of age), including infliximab products. Approximately half of these cases were lymphomas, including Hodgkin's and non-Hodgkin's lymphoma. The other cases represented a variety of malignancies, including rare malignancies that are usually associated with immunosuppression and malignancies that are not usually observed in children and adolescents. The malignancies occurred after a median of 30 months (range 1 to 84 months) after the first dose of TNF blocker therapy. Most of the patients were receiving concomitant immunosuppressants. These cases were reported postmarketing and are derived from a variety of sources, including registries and spontaneous postmarketing reports.

Lymphomas

In the controlled portions of clinical trials of all the TNF blockers, more cases of lymphoma have been observed among patients receiving a TNF blocker compared with control patients. In the controlled and open-label portions of infliximab clinical trials, 5 patients developed lymphomas among 5707 patients treated with infliximab (median duration of follow-up 1.0 years) vs. 0 lymphomas in 1600 control patients (median duration of follow-up 0.4 years). In RA patients, 2 lymphomas were observed for a rate of 0.08 cases per 100 patient-years of follow-up, which is approximately three-fold higher than expected in the general population. In the combined clinical trial population for RA, CD, PsA, AS, UC, and Ps, 5 lymphomas were observed for a rate of 0.10 cases per 100 patient-years of follow-up, which is approximately four-fold higher than expected in the general population. Patients with CD, RA or Ps, particularly patients with highly active disease and/or chronic exposure to immunosuppressant therapies, may be at a higher risk (up to several fold) than the general population for the development of lymphoma, even in the absence of TNF blockers. Cases of acute and chronic leukemia have been reported with postmarketing TNF blocker use in RA and other diseases. Even in the absence of TNF blocker therapy, patients with RA may be at a higher risk (approximately 2-fold) than the general population for the development of leukemia.

Hepatosplenic T-cell Lymphoma (HSTCL)

Postmarketing cases of hepatosplenic T-cell lymphoma (HSTCL), a rare type of T-cell lymphoma, have been reported in patients treated with TNF blockers including infliximab products. These cases have had a very aggressive disease course and have been fatal. Almost all patients had received treatment with the immunosuppressants azathioprine or 6-mercaptopurine concomitantly with a TNF blocker at or prior to diagnosis. The majority of reported cases have occurred in patients with CD or UC and most were in adolescent and young adult males. It is uncertain whether the occurrence of HSTCL is related to TNF blockers or TNF blockers in combination with these other immunosuppressants. When treating patients, consideration of whether to use AVSOLA alone or in combination with other immunosuppressants such as azathioprine or 6-mercaptopurine should take into account a possibility that there is a higher risk of HSTCL with combination therapy versus an observed increased risk of immunogenicity and hypersensitivity reactions with infliximab product monotherapy from the clinical trial data from studies with infliximab [see Warnings and Precautions (5.7) and Adverse Reactions (6.1)].

Skin Cancer

Melanoma and Merkel cell carcinoma have been reported in patients treated with TNF blocker therapy, including infliximab products [see Adverse Reactions (6.3)]. Periodic skin examination is recommended for all patients, particularly those with risk factors for skin cancer.

Cervical Cancer

A population-based retrospective cohort study using data from Swedish national health registries found a 2- to 3-fold increase in the incidence of invasive cervical cancer in women with RA treated with infliximab compared to biologics-naïve patients or the general population, particularly those over 60 years of age. A causal relationship between infliximab products and cervical cancer cannot be excluded. Periodic screening should continue in women treated with AVSOLA [see Adverse Reactions (6.3)].

Other Malignancies

In the controlled portions of clinical trials of some TNF blockers including infliximab products, more malignancies (excluding lymphoma and nonmelanoma skin cancer [NMSC]) have been observed in patients receiving those TNF blockers compared with control patients. During the controlled portions of trials with infliximab, in patients with moderately to severely active RA, CD, PsA, AS, UC, and Ps, 14 patients were diagnosed with malignancies (excluding lymphoma and NMSC) among 4019 infliximab-treated patients vs. 1 among 1597 control patients (at a rate of 0.52/100 patient-years among infliximab-treated patients vs. a rate of 0.11/100 patient-years among control patients), with median duration of follow-up 0.5 years for infliximab-treated patients and 0.4 years for control patients. Of these, the most common malignancies were breast, colorectal, and melanoma. The rate of malignancies among infliximab-treated patients was similar to that expected in the general population whereas the rate in control patients was lower than expected.

In a clinical trial exploring the use of infliximab in patients with moderate to severe chronic obstructive pulmonary disease (COPD), more malignancies, the majority of lung or head and neck origin, were reported in infliximab-treated patients compared with control patients. All patients had a history of heavy smoking [see Adverse Reactions (6.1)]. Prescribers should exercise caution when considering the use of AVSOLA in patients with moderate to severe COPD.

Ps patients should be monitored for nonmelanoma skin cancers (NMSCs), particularly those patients who have had prior prolonged phototherapy treatment. In the maintenance portion of clinical trials for infliximab, NMSCs were more common in patients with previous phototherapy [see Adverse Reactions (6.1)].

The potential role of TNF blockers in the development of malignancies is not known [see Adverse Reactions (6.1)]. Rates in clinical trials for infliximab cannot be compared to rates in clinical trials of other TNF blockers and may not predict rates observed in a broader patient population. Caution should be exercised in considering AVSOLA treatment in patients with a history of malignancy or in continuing treatment in patients who develop malignancy while receiving AVSOLA.

5.3 Hepatitis B Virus Reactivation

Use of TNF blockers, including infliximab products, has been associated with reactivation of hepatitis B virus (HBV) in patients who are chronic carriers of this virus. In some instances, HBV reactivation occurring in conjunction with TNF blocker therapy has been fatal. The majority of these reports have occurred in patients concomitantly receiving other medications that suppress the immune system, which may also contribute to HBV reactivation. Patients should be tested for HBV infection before initiating TNF blocker therapy, including AVSOLA. For patients who test positive for hepatitis B surface antigen, consultation with a physician with expertise in the treatment of hepatitis B is recommended. Adequate data are not available on the safety or efficacy of treating patients who are carriers of HBV with anti-viral therapy in conjunction with TNF blocker therapy to prevent HBV reactivation. Patients who are carriers of HBV and require treatment with TNF blockers should be closely monitored for clinical and laboratory signs of active HBV infection throughout therapy and for several months following termination of therapy. In patients who develop HBV reactivation, TNF blockers should be stopped and anti-viral therapy with appropriate supportive treatment should be initiated. The safety of resuming TNF blocker therapy after HBV reactivation is controlled is not known. Therefore, prescribers should exercise caution when considering resumption of TNF blocker therapy in this situation and monitor patients closely.

5.4 Hepatotoxicity

Severe hepatic reactions, including acute liver failure, jaundice, hepatitis and cholestasis, have been reported in postmarketing data in patients receiving infliximab products. Autoimmune hepatitis has been diagnosed in some of these cases. Severe hepatic reactions occurred between 2 weeks to more than 1-year after initiation of infliximab products; elevations in hepatic aminotransferase levels were not noted prior to discovery of the liver injury in many of these cases. Some of these cases were fatal or necessitated liver transplantation. Patients with symptoms or signs of liver dysfunction should be evaluated for evidence of liver injury. If jaundice and/or marked liver enzyme elevations (e.g., ≥5 times the upper limit of normal) develop, AVSOLA should be discontinued, and a thorough investigation of the abnormality should be undertaken. In clinical trials, mild or moderate elevations of ALT and AST have been observed in patients receiving infliximab products without progression to severe hepatic injury [see Adverse Reactions (6.1)].

5.5 Heart Failure

The use of AVSOLA at doses >5 mg/kg is contraindicated in patients with moderate or severe heart failure. A randomized, double-blind, placebo-controlled study evaluated the use of infliximab (5 mg/kg or 10 mg/kg at Weeks 0, 2, and 6) in patients with moderate or severe heart failure [New York Heart Association (NYHA) Functional Class III/IV]. Compared to patients who received placebo, there was a higher rate of mortality and a higher risk of hospitalization at Week 28 due to heart failure in patients who received the 10 mg/kg infliximab dose, and higher rates of cardiovascular adverse events in patients who received infliximab doses of 5 mg/kg and 10 mg/kg.

There have been post-marketing reports of new onset and worsening heart failure, with and without identifiable precipitating factors (e.g., pre-existing cardiovascular disease), in patients treated with infliximab products. Some of these patients have been under 50 years of age.

If a decision is made to administer AVSOLA (≤5 mg/kg) to patients with moderate or severe heart failure or to administer AVSOLA (any approved dose) to patients with mild heart failure, they should be closely monitored during therapy, and AVSOLA should be discontinued if new or worsening symptoms of heart failure appear [see Contraindications (4) and Adverse Reactions (6.1)].

5.6 Hematologic Reactions

Cases of leukopenia, neutropenia, thrombocytopenia, and pancytopenia, some with a fatal outcome, have been reported in patients receiving infliximab products. The causal relationship to infliximab product therapy remains unclear. Although no high-risk group(s) has been identified, caution should be exercised in patients being treated with AVSOLA who have ongoing or a history of significant hematologic abnormalities. All patients should be advised to seek immediate medical attention if they develop signs and symptoms suggestive of blood dyscrasias or infection (e.g., persistent fever) while on AVSOLA. Discontinuation of AVSOLA therapy should be considered in patients who develop significant hematologic abnormalities.

5.7 Hypersensitivity

Infliximab products have been associated with hypersensitivity reactions that vary in their time of onset and required hospitalization in some cases. Most hypersensitivity reactions (including anaphylaxis, urticaria, dyspnea, and/or hypotension), have occurred during or within 2 hours of infliximab product infusion.

However, in some cases, serum sickness-like reactions have been observed in patients after initial therapy with infliximab products (i.e., as early as after the second dose), and when therapy with infliximab products was reinstituted following an extended period without treatment. Symptoms associated with these reactions include fever, rash, headache, sore throat, myalgias, polyarthralgias, hand and facial edema and/or dysphagia. These reactions were associated with a marked increase in antibodies to infliximab products, loss of detectable serum concentrations of infliximab products, and possible loss of drug efficacy.

AVSOLA should be discontinued for severe hypersensitivity reactions. Medications for the treatment of hypersensitivity reactions (e.g., acetaminophen, antihistamines, corticosteroids and/or epinephrine) should be available for immediate use in the event of a reaction [see Dosage and Administration (2.10) and Adverse Reactions (6.1)].

In RA, CD and Ps clinical trials, re-administration of infliximab after a period of no treatment resulted in a higher incidence of infusion reactions relative to regular maintenance treatment [see Adverse Reactions (6.1)]. In general, the benefit-risk of re-administration of AVSOLA after a period of no-treatment, especially as a re-induction regimen given at Weeks 0, 2 and 6, should be carefully considered. In the case where AVSOLA maintenance therapy for Ps is interrupted, AVSOLA should be reinitiated as a single-dose followed by maintenance therapy.

5.8 Cardiovascular and Cerebrovascular Reactions During and After Infusion

Serious cerebrovascular accidents, myocardial ischemia/infarction (some fatal), hypotension, hypertension, and arrhythmias have been reported during and within 24 hours of initiation of infliximab product infusion. Cases of transient visual loss have been reported during or within 2 hours of infliximab product infusion. Monitor patients during infusion and if serious reaction occurs, discontinue infusion. Further management of reactions should be dictated by signs and symptoms [see Adverse Reactions (6)].

5.9 Neurologic Reactions

Agents that inhibit TNF have been associated with CNS manifestation of systemic vasculitis, seizure and new onset or exacerbation of clinical symptoms and/or radiographic evidence of central nervous system demyelinating disorders, including multiple sclerosis and optic neuritis, and peripheral demyelinating disorders, including Guillain-Barré syndrome. Prescribers should exercise caution in considering the use of AVSOLA in patients with these neurologic disorders and should consider discontinuation of AVSOLA if these disorders develop.

5.10 Concurrent Administration with Other Biological Products

Serious infections and neutropenia were seen in clinical studies with concurrent use of anakinra and another TNF blocker, etanercept, with no added clinical benefit compared to etanercept alone. Because of the nature of the adverse reactions seen with the concurrent use of etanercept and anakinra therapy, similar toxicities may also result from the concurrent use of anakinra and other TNF blockers. Therefore, the concurrent use of AVSOLA and anakinra is not recommended.

In clinical studies, concurrent administration of TNF blockers and abatacept have been associated with an increased risk of infections including serious infections compared with TNF blockers alone, without increased clinical benefit. Therefore, the concurrent use of AVSOLA and abatacept is not recommended [see Drug Interactions (7.1)].

There is insufficient information regarding the concurrent use of infliximab products with other biological products used to treat the same conditions as AVSOLA. The concurrent use of AVSOLA with these biological products is not recommended because of the possibility of an increased risk of infection [see Drug Interactions (7.1)].

5.11 Switching Between Biological Disease-Modifying Antirheumatic Drugs (DMARDs)

Care should be taken when switching from one biologic to another, since overlapping biological activity may further increase the risk of infection.

5.12 Autoimmunity

Treatment with infliximab products may result in the formation of autoantibodies and in the development of a lupus-like syndrome. If a patient develops symptoms suggestive of a lupus-like syndrome following treatment with AVSOLA, treatment should be discontinued [see Adverse Reactions (6.1)].

5.13 Vaccinations and Use of Live Vaccines/Therapeutic Infectious Agents

Vaccinations

Prior to initiating AVSOLA in pediatric and adult patients, update vaccinations in accordance with current vaccination guidelines.

Live Vaccines and Therapeutic Infectious Agents

In patients receiving TNF blockers, limited data are available on the response to vaccination with live vaccines or on the secondary transmission of infection by live vaccines. Use of live vaccines can result in clinical infections, including disseminated infections. The concurrent administration of live vaccines with AVSOLA is not recommended.

Fatal outcome due to disseminated BCG infection has been reported in an infant who received a BCG vaccine after in utero exposure to infliximab products. Infliximab products are known to cross the placenta and have been detected up to 6 months following birth. At least a six-month waiting period following birth is recommended before the administration of any live vaccine to infants exposed in utero to infliximab products.

Other uses of therapeutic infectious agents such as live attenuated bacteria (e.g., BCG bladder instillation for the treatment of cancer) could result in clinical infections, including disseminated infections. It is recommended that therapeutic infectious agents not be given concurrently with AVSOLA.

6 ADVERSE REACTIONS

6.1 Clinical Trials Experience

Because clinical trials are conducted under widely varying conditions, adverse reaction rates observed in the clinical trials of a drug cannot be directly compared to rates in the clinical trials of another drug and may not reflect the rates observed in practice.

Adverse Reactions in Adults

The data described herein reflect exposure to infliximab in 4779 adult patients (1304 patients with RA, 1106 patients with CD, 202 with AS, 293 with PsA, 484 with UC, 1373 with Ps, and 17 patients with other conditions), including 2625 patients exposed beyond 30 weeks and 374 exposed beyond 1-year. [For information on adverse reactions in pediatric patients, see Adverse Reactions (6.1)]. One of the most common reasons for discontinuation of treatment was infusion-related reactions (e.g., dyspnea, flushing, headache and rash).

Infusion-Related Reactions

Adverse Reactions During or Shortly After Infusion

An infusion reaction was defined in clinical trials as any adverse event occurring during an infusion or within 1 hour after an infusion. In all the clinical studies, approximately 20% of infliximab-treated patients experienced an infusion reaction compared with 10% of placebo-treated patients. Of infliximab-treated patients who had an infusion reaction during the induction period, 27% experienced an infusion reaction during the maintenance period. Of patients who did not have an infusion reaction during the induction period, 9% experienced an infusion reaction during the maintenance period.

Among all infliximab infusions, 3% were accompanied by nonspecific symptoms such as fever or chills, 1% were accompanied by cardiopulmonary reactions (primarily chest pain, hypotension, hypertension or dyspnea), and <1% were accompanied by pruritus, urticaria, or the combined symptoms of pruritus/urticaria and cardiopulmonary reactions. Serious infusion reactions occurred in <1% of patients and included anaphylaxis, convulsions, erythematous rash and hypotension. Approximately 3% of patients discontinued infliximab treatment because of infusion reactions, and all patients recovered with treatment and/or discontinuation of the infusion. Infliximab infusions beyond the initial infusion were not associated with a higher incidence of reactions. The infusion reaction rates remained stable in Ps through 1-year in Ps Study I. In Ps Study II, the rates were variable over time and somewhat higher following the final infusion than after the initial infusion. Across the 3 Ps studies, the percent of total infusions resulting in infusion reactions (i.e., an adverse event occurring within 1 hour) was 7% in the 3 mg/kg group, 4% in the 5 mg/kg group, and 1% in the placebo group.

Patients who became positive for antibodies to infliximab were more likely (approximately two- to three-fold) to have an infusion reaction than were those who were negative. Use of concomitant immunosuppressant agents appeared to reduce the frequency of both antibodies to infliximab and infusion reactions [see Adverse Reactions (6.2) and Drug Interactions (7.3)].

Infusion Reactions Following Re-administration

In a clinical trial of patients with moderate to severe Ps designed to assess the efficacy of long-term maintenance therapy versus re-treatment with an induction regimen of infliximab following disease flare, 4% (8/219) of patients in the re-treatment induction therapy arm experienced serious infusion reactions versus <1% (1/222) in the maintenance therapy arm. Patients enrolled in this trial did not receive any concomitant immunosuppressant therapy. In this study, the majority of serious infusion reactions occurred during the second infusion at Week 2. Symptoms included, but were not limited to, dyspnea, urticaria, facial edema, and hypotension. In all cases, treatment with infliximab was discontinued and/or other treatment instituted with complete resolution of signs and symptoms.

Delayed Reactions/Reactions Following Re-administration

In Ps studies, approximately 1% of infliximab-treated patients experienced a possible delayed hypersensitivity reaction, generally reported as serum sickness or a combination of arthralgia and/or myalgia with fever and/or rash. These reactions generally occurred within 2 weeks after repeat infusion.

Infections

In infliximab clinical studies, treated infections were reported in 36% of infliximab-treated patients (average of 51 weeks of follow-up) and in 25% of placebo-treated patients (average of 37 weeks of follow-up). The infections most frequently reported were respiratory tract infections (including sinusitis, pharyngitis, and bronchitis) and urinary tract infections. Among infliximab-treated patients, serious infections included pneumonia, cellulitis, abscess, skin ulceration, sepsis, and bacterial infection. In clinical trials, 7 opportunistic infections were reported; 2 cases each of coccidioidomycosis (1 case was fatal) and histoplasmosis (1 case was fatal), and 1 case each of pneumocystosis, nocardiosis and cytomegalovirus. Tuberculosis (TB) was reported in 14 patients, 4 of whom died due to miliary TB. Other cases of TB, including disseminated TB, also have been reported postmarketing. Most of these cases of TB occurred within the first 2 months after initiation of therapy with infliximab and may reflect recrudescence of latent disease [see Warnings and Precautions (5.1)]. In the 1-year placebo-controlled studies RA I and RA II, 5.3% of patients receiving infliximab every 8 weeks with MTX developed serious infections as compared to 3.4% of placebo patients receiving MTX. Of 924 patients receiving infliximab, 1.7% developed pneumonia and 0.4% developed TB, when compared to 0.3% and 0.0% in the placebo arm respectively. In a shorter (22-week) placebo-controlled study of 1082 RA patients randomized to receive placebo, 3 mg/kg or 10 mg/kg infliximab infusions at 0, 2, and 6 weeks, followed by every 8 weeks with MTX, serious infections were more frequent in the 10 mg/kg infliximab group (5.3%) than the 3 mg/kg or placebo groups (1.7% in both). During the 54-week Crohn's II Study, 15% of patients with fistulizing CD developed a new fistula-related abscess.

In infliximab clinical studies in patients with UC, infections treated with antimicrobials were reported in 27% of infliximab-treated patients (average of 41 weeks of follow-up) and in 18% of placebo-treated patients (average 32 weeks of follow-up). The types of infections, including serious infections, reported in patients with UC were similar to those reported in other clinical studies.

The onset of serious infections may be preceded by constitutional symptoms such as fever, chills, weight loss, and fatigue. The majority of serious infections, however, may also be preceded by signs or symptoms localized to the site of the infection.

Autoantibodies/Lupus-like Syndrome

Approximately half of the infliximab-treated patients in clinical trials who were antinuclear antibody (ANA) negative at baseline developed a positive ANA during the trial compared with approximately one-fifth of placebo-treated patients. Anti-dsDNA antibodies were newly detected in approximately one-fifth of infliximab-treated patients compared with 0% of placebo-treated patients. Reports of lupus and lupus-like syndromes, however, remain uncommon.

Malignancies

In controlled trials, more infliximab-treated patients developed malignancies than placebo-treated patients [see Warnings and Precautions (5.2)].

In a randomized controlled clinical trial exploring the use of infliximab in patients with moderate to severe COPD who were either current smokers or ex-smokers, 157 patients were treated with infliximab at doses similar to those used in RA and CD. Of these infliximab-treated patients, 9 developed a malignancy, including 1 lymphoma, for a rate of 7.67 cases per 100 patient-years of follow-up (median duration of follow-up 0.8 years; 95% CI 3.51 - 14.56). There was 1 reported malignancy among 77 control patients for a rate of 1.63 cases per 100 patient-years of follow-up (median duration of follow-up 0.8 years; 95% CI 0.04 - 9.10). The majority of the malignancies developed in the lung or head and neck [see Warnings and Precautions (5.2)].

Adverse Reactions in Patients with NYHA Class III/IV Heart Failure

In a randomized, double-blind study evaluating infliximab in moderate or severe heart failure (NYHA Class III/IV; left ventricular ejection fraction ≤35%), 150 patients were randomized to receive treatment with 3 infusions of infliximab 10 mg/kg, 5 mg/kg, or placebo, at 0, 2, and 6 weeks. Higher incidences of mortality and hospitalization due to worsening heart failure were observed in patients receiving the 10 mg/kg infliximab dose. At 1 year, 8 patients in the 10 mg/kg infliximab group had died compared with 4 deaths each in the 5 mg/kg infliximab and the placebo groups. There were trends toward increased dyspnea, hypotension, angina, and dizziness in both the 10 mg/kg and 5 mg/kg infliximab treatment groups, versus placebo. Infliximab products have not been studied in patients with mild heart failure (NYHA Class I/II) [see Contraindications (4) and Warnings and Precautions (5.5)].

Hepatotoxicity

Severe liver injury, including acute liver failure and autoimmune hepatitis, has been reported in patients receiving infliximab products [see Warnings and Precautions (5.4)]. Reactivation of hepatitis B virus has occurred in patients receiving TNF blockers, including infliximab products, who are chronic carriers of this virus [see Warnings and Precautions (5.3)].

In clinical trials in RA, CD, UC, AS, Ps, and PsA, elevations of aminotransferases were observed (ALT more common than AST) in a greater proportion of patients receiving infliximab than in controls (Table 1), both when infliximab was given as monotherapy and when it was used in combination with other immunosuppressive agents. In general, patients who developed ALT and AST elevations were asymptomatic, and the abnormalities decreased or resolved with either continuation or discontinuation of infliximab, or modification of concomitant medications.

Table 1: Proportion of Patients with Elevated ALT in Clinical Trials in Adults
 | Proportion of patients with elevated ALT
 | >1 to <3 × ULN |  | ≥3 × ULN |  | ≥5 × ULN
 | Placebo | Infliximab | Placebo | Infliximab | Placebo | Infliximab
Rheumatoid arthritis [Placebo patients received methotrexate while patients treated with infliximab received both infliximab and methotrexate. Median follow-up was 58 weeks.] | 24% | 34% | 3% | 4% | <1% | <1%
Crohn's disease [Placebo patients in the 2 Phase 3 trials in CD received an initial dose of 5 mg/kg infliximab at study start and were on placebo in the maintenance phase. Patients who were randomized to the placebo maintenance group and then later crossed over to infliximab are included in the infliximab group in ALT analysis. Median follow-up was 54 weeks.] | 34% | 39% | 4% | 5% | 0% | 2%
Ulcerative colitis [Median follow-up was 30 weeks. Specifically, the median duration of follow-up was 30 weeks for placebo and 31 weeks for infliximab.] | 12% | 17% | 1% | 2% | <1% | <1%
Ankylosing spondylitis [Median follow-up was 24 weeks for the placebo group and 102 weeks for the infliximab group.] | 15% | 51% | 0% | 10% | 0% | 4%
Psoriatic arthritis [Median follow-up was 39 weeks for the infliximab group and 18 weeks for the placebo group.] | 16% | 50% | 0% | 7% | 0% | 2%
Plaque psoriasis [ALT values are obtained in 2 Phase 3 Ps studies with median follow-up of 50 weeks for infliximab and 16 weeks for placebo.] | 24% | 49% | <1% | 8% | 0% | 3%

Adverse Reactions in Psoriasis Studies

During the placebo-controlled portion across the 3 clinical trials up to Week 16, the proportion of patients who experienced at least 1 serious adverse reaction (SAE; defined as resulting in death, life threatening, requires hospitalization, or persistent or significant disability/incapacity) was 0.5% in the 3 mg/kg infliximab group, 1.9% in the placebo group, and 1.6% in the 5 mg/kg infliximab group.

Among patients in the 2 Phase 3 studies, 12.4% of patients receiving infliximab 5 mg/kg every 8 weeks through 1-year of maintenance treatment experienced at least 1 SAE in Study I. In Study II, 4.1% and 4.7% of patients receiving infliximab 3 mg/kg and 5 mg/kg every 8 weeks, respectively, through 1-year of maintenance treatment experienced at least 1 SAE.

One death due to bacterial sepsis occurred 25 days after the second infusion of 5 mg/kg infliximab. Serious infections included sepsis, and abscesses. In Study I, 2.7% of patients receiving infliximab 5 mg/kg every 8 weeks through 1-year of maintenance treatment experienced at least 1 serious infection. In Study II, 1.0% and 1.3% of patients receiving infliximab 3 mg/kg and 5 mg/kg, respectively, through 1-year of treatment experienced at least 1 serious infection. The most common serious infection (requiring hospitalization) was abscess (skin, throat, and peri-rectal) reported by 5 (0.7%) patients in the 5 mg/kg infliximab group. Two active cases of tuberculosis were reported: 6 weeks and 34 weeks after starting infliximab.

In the placebo-controlled portion of the Ps studies, 7 of 1123 patients who received infliximab at any dose were diagnosed with at least one NMSC compared to 0 of 334 patients who received placebo.

In the Ps studies, 1% (15/1373) of patients experienced serum sickness or a combination of arthralgia and/or myalgia with fever, and/or rash, usually early in the treatment course. Of these patients, 6 required hospitalization due to fever, severe myalgia, arthralgia, swollen joints, and immobility.

Other Adverse Reactions in Adults

Safety data are available from 4779 infliximab-treated adult patients, including 1304 with RA, 1106 with CD, 484 with UC, 202 with AS, 293 with PsA, 1373 with Ps and 17 with other conditions. [For information on other adverse reactions in pediatric patients, see Adverse Reactions (6.1)]. Adverse reactions reported in ≥5% of all patients with RA receiving 4 or more infusions are in Table 2. The types and frequencies of adverse reactions observed were similar in RA, AS, PsA, Ps and CD patients treated with infliximab except for abdominal pain, which occurred in 26% of infliximab-treated patients with CD. In the CD studies, there were insufficient numbers and duration of follow-up for patients who never received infliximab to provide meaningful comparisons.

Table 2: Adverse Reactions that Occurred in ≥ 5% of Patients who Received ≥4 Infliximab Infusions for RA
 | Placebo | Infliximab
 | (n=350) | (n=1129)
Average weeks of follow-up | 59 weeks | 66 weeks
Upper respiratory tract infection | 25% | 32%
Nausea | 20% | 21%
Headache | 14% | 18%
Sinusitis | 8% | 14%
Diarrhea | 12% | 12%
Abdominal pain | 8% | 12%
Pharyngitis | 8% | 12%
Coughing | 8% | 12%
Bronchitis | 9% | 10%
Rash | 5% | 10%
Dyspepsia | 7% | 10%
Fatigue | 7% | 9%
Urinary tract infection | 6% | 8%
Pain | 7% | 8%
Arthralgia | 7% | 8%
Pruritus | 2% | 7%
Fever | 4% | 7%
Hypertension | 5% | 7%
Moniliasis | 3% | 5%

The most common serious adverse reactions observed in clinical trials were infections [see Adverse Reactions (6.1)]. Other serious, medically relevant adverse reactions ≥0.2% or clinically significant adverse reactions by body system were as follows:

- Body as a whole: allergic reaction, edema
- Blood: pancytopenia
- Cardiovascular: hypotension
- Gastrointestinal: constipation, intestinal obstruction
- Central and Peripheral Nervous: dizziness
- Heart Rate and Rhythm: bradycardia
- Liver and Biliary: hepatitis
- Metabolic and Nutritional: dehydration
- Platelet, Bleeding and Clotting: thrombocytopenia
- Neoplasms: lymphoma
- Red Blood Cell: anemia, hemolytic anemia
- Resistance Mechanism: cellulitis, sepsis, serum sickness, sarcoidosis
- Respiratory: lower respiratory tract infection (including pneumonia), pleurisy, pulmonary edema
- Skin and Appendages: increased sweating
- Vascular (Extracardiac): thrombophlebitis
- White Cell and Reticuloendothelial: leukopenia, lymphadenopathy

Adverse Reactions in Pediatric Patients

Adverse Reactions in Pediatric Patients with Crohn's Disease

There were some differences in the adverse reactions observed in the pediatric patients receiving infliximab compared to those observed in adults with CD. These differences are discussed in the following paragraphs.

The following adverse reactions were reported more commonly in 103 randomized pediatric CD patients administered 5 mg/kg infliximab through 54 weeks than in 385 adult CD patients receiving a similar treatment regimen: anemia (11%), leukopenia (9%), flushing (9%), viral infection (8%), neutropenia (7%), bone fracture (7%), bacterial infection (6%), and respiratory tract allergic reaction (6%).

Infections were reported in 56% of randomized pediatric patients in Study Peds Crohn's and in 50% of adult patients in Study Crohn's I. In Study Peds Crohn's, infections were reported more frequently for patients who received every 8-week as opposed to every 12-week infusions (74% and 38%, respectively), while serious infections were reported for 3 patients in the every 8-week and 4 patients in the every 12-week maintenance treatment group. The most commonly reported infections were upper respiratory tract infection and pharyngitis, and the most commonly reported serious infection was abscess. Pneumonia was reported for 3 patients, (2 in the every 8-week and 1 in the every 12-week maintenance treatment groups). Herpes zoster was reported for 2 patients in the every 8-week maintenance treatment group.

In Study Peds Crohn's, 18% of randomized patients experienced 1 or more infusion reactions, with no notable difference between treatment groups. Of the 112 patients in Study Peds Crohn's, there were no serious infusion reactions, and 2 patients had non-serious anaphylactoid reactions.

Elevations of ALT up to 3 times the upper limit of normal (ULN) were seen in 18% of pediatric patients in CD clinical trials; 4% had ALT elevations ≥3 × ULN, and 1% had elevations ≥5 × ULN. (Median follow-up was 53 weeks).

Adverse Reactions in Pediatric Patients with Ulcerative Colitis

Overall, the adverse reactions reported in the pediatric UC trial and adult UC (Study UC I and Study UC II) studies were generally consistent. In a pediatric UC trial, the most common adverse reactions were upper respiratory tract infection, pharyngitis, abdominal pain, fever, and headache.

Infections were reported in 31 (52%) of 60 treated patients in the pediatric UC trial and 22 (37%) required oral or parenteral antimicrobial treatment. The proportion of patients with infections in the pediatric UC trial was similar to that in the pediatric CD study (Study Peds Crohn's) but higher than the proportion in the adults' UC studies (Study UC I and Study UC II). The overall incidence of infections in the pediatric UC trial was 13/22 (59%) in the every 8-week maintenance treatment group. Upper respiratory tract infection (7/60 [12%]) and pharyngitis (5/60 [8%]) were the most frequently reported respiratory system infections. Serious infections were reported in 12% (7/60) of all treated patients.

Elevations of ALT up to 3 times the upper limit of normal (ULN) were seen in 17% (10/60) of pediatric patients in the pediatric UC trial; 7% (4/60) had ALT elevations ≥3 × ULN, and 2% (1/60) had elevations ≥5 × ULN (median follow-up was 49 weeks).

Overall, 8 of 60 (13%) treated patients experienced one or more infusion reactions, including 4 of 22 (18%) patients in the every 8-week treatment maintenance group. No serious infusion reactions were reported.

In the pediatric UC trial, 45 patients were in the 12- to 17-year age group and 15 in the 6- to 11-year age group. The numbers of patients in each subgroup are too small to make any definitive conclusions about the effect of age on safety events. There were higher proportions of patients with serious adverse events (40% vs. 18%) and discontinuation due to adverse events (40% vs. 16%) in the younger age group than in the older age group. While the proportion of patients with infections was also higher in the younger age group (60% vs. 49%), for serious infections, the proportions were similar in the two age groups (13% in the 6- to 11-year age group vs. 11% in the 12- to 17-year age group). Overall proportions of adverse reactions, including infusion reactions, were similar between the 6- to 11- and 12- to 17-year age groups (13%).

6.2 Immunogenicity

The observed incidence of anti-drug antibodies is highly dependent on the sensitivity and specificity of the assay. Differences in assay methods preclude meaningful comparisons of the incidence of anti-drug antibodies in the studies described below with the incidence of anti-drug antibodies in other studies, including those of infliximab or of other infliximab products.

Treatment with infliximab products can be associated with the development of antibodies to infliximab products. An enzyme immunoassay (EIA) method was originally used to measure anti-infliximab antibodies in clinical studies of infliximab. The EIA method is subject to interference by serum infliximab, possibly resulting in an underestimation of the rate of patient antibody formation. A separate, drug-tolerant electrochemiluminescence immunoassay (ECLIA) method for detecting antibodies to infliximab was subsequently developed and validated. This method is 60-fold more sensitive than the original EIA. With the ECLIA method, all clinical samples can be classified as either positive or negative for antibodies to infliximab without the need for the inconclusive category.

The incidence of antibodies to infliximab was based on the original EIA method in all clinical studies of infliximab except for the Phase 3 study in pediatric patients with UC where the incidence of antibodies to infliximab was detected using both the EIA and ECLIA methods.

Immunogenicity in Adult Patients

The incidence of antibodies to infliximab in patients with RA and CD given a 3-dose induction regimen followed by maintenance dosing was approximately 10% as assessed through 1 to 2 years of treatment with infliximab. A higher incidence of antibodies to infliximab was observed in CD patients receiving infliximab after drug-free intervals >16 weeks. In a study of PsA in which 191 patients received 5 mg/kg with or without MTX, antibodies to infliximab occurred in 15% of patients. The majority of antibody-positive patients had low titers. Antibody development was lower among RA and CD patients receiving immunosuppressant therapies such as 6-MP/AZA or MTX. Patients who were antibody-positive were more likely to have higher rates of clearance, have reduced efficacy and to experience an infusion reaction than were patients who were antibody negative [see Adverse Reactions (6.1)]. In the Ps Study II, which included both the 5 mg/kg and 3 mg/kg doses, antibodies were observed in 36% of patients treated with 5 mg/kg every 8 weeks for 1 year, and in 51% of patients treated with 3 mg/kg every 8 weeks for 1 year.

In the Ps Study III, which also included both the 5 mg/kg and 3 mg/kg doses, antibodies were observed in 20% of patients treated with 5 mg/kg induction (Weeks 0, 2 and 6), and in 27% of patients treated with 3 mg/kg induction. Despite the increase in antibody formation, the infusion reaction rates in Studies I and II in patients treated with 5 mg/kg induction followed by every 8-week maintenance for 1-year and in Study III in patients treated with 5 mg/kg induction (14.1%-23.0%) and serious infusion reaction rates (<1%) were similar to those observed in other study populations. The clinical significance of apparent increased immunogenicity on efficacy and infusion reactions in Ps patients as compared to patients with other diseases treated with infliximab products over the long-term is not known.

Immunogenicity in Pediatric Patients with Crohn's Disease

In Study Peds Crohn's, in which all patients received stable doses of 6-MP, AZA, or MTX, excluding inconclusive samples, 3 of 24 patients had antibodies to infliximab. Although 105 patients were tested for antibodies to infliximab, 81 patients were classified as inconclusive because they could not be ruled as negative due to assay interference by the presence of infliximab in the sample.

Immunogenicity in Pediatric Patients with Ulcerative Colitis

In the pediatric UC trial, 58 patients were evaluated for antibodies to infliximab using the EIA as well as the drug-tolerant ECLIA. With the EIA, 4 of 58 (7%) patients had antibodies to infliximab. With the ECLIA, 30 of 58 (52%) patients had antibodies to infliximab. The higher incidence of antibodies to infliximab by the ECLIA method was due to the 60-fold higher sensitivity compared to the EIA method. While EIA-positive patients generally had undetectable trough infliximab concentrations, ECLIA-positive patients could have detectable trough concentrations of infliximab because the ECLIA assay is more sensitive and drug-tolerant.

6.3 Postmarketing Experience

Adverse reactions, some with fatal outcomes, have been identified during post-approval use of infliximab products in adult and pediatric patients. Because these reactions are reported voluntarily from a population of uncertain size, it is not always possible to reliably estimate their frequency or establish a causal relationship to drug exposure.

Postmarketing Adverse Reactions in Adults and Pediatric Patients

- Neutropenia [see Warnings and Precautions (5.6)], agranulocytosis (including infants exposed in utero to infliximab products), idiopathic thrombocytopenic purpura, thrombotic thrombocytopenic purpura.
- Interstitial lung disease (including pulmonary fibrosis/interstitial pneumonitis and rapidly progressive disease).
- Pericardial effusion, systemic and cutaneous vasculitis.
- Erythema multiforme, Stevens-Johnson Syndrome, toxic epidermal necrolysis, linear IgA bullous dermatosis (LABD), acute generalized exanthematous pustulosis (AGEP), worsening psoriasis (all subtypes including pustular, primarily palmoplantar), lichenoid reactions.
- Peripheral demyelinating disorders (such as Guillain-Barré syndrome, chronic inflammatory demyelinating polyneuropathy, and multifocal motor neuropathy) transverse myelitis, and neuropathies (additional neurologic reactions have also been observed) [see Warnings and Precautions (5.9)].
- Acute liver failure, jaundice, hepatitis, and cholestasis [see Warnings and Precautions (5.4)].
- Serious infections [see Warnings and Precautions (5.1)] and vaccine breakthrough infection including bovine tuberculosis (disseminated BCG infection) following vaccination in an infant exposed in utero to infliximab products [see Warnings and Precautions (5.13)].
- Malignancies, including leukemia, melanoma, Merkel cell carcinoma, and cervical cancer [see Warnings and Precautions (5.2)].
- Anaphylactic reactions, including anaphylactic shock, laryngeal/pharyngeal edema and severe bronchospasm, and seizure have been associated with administration of infliximab products.
- Transient visual loss have been reported in association with infliximab products during or within 2 hours of infusion. Cerebrovascular accidents, myocardial ischemia/infarction (some fatal), and arrhythmia occurring within 24 hours of initiation of infusion have also been reported [see Warnings and Precautions (5.8)].
- New onset immune disorders (e.g., psoriasis, rheumatoid arthritis, inflammatory bowel disease).

Postmarketing Serious Adverse Reactions in Pediatric Patients

The following serious adverse reactions have been reported in the postmarketing experience in pediatric patients: infections (some fatal) including opportunistic infections and tuberculosis, infusion reactions, hypersensitivity reactions, malignancies, including hepatosplenic T-cell lymphomas [see Boxed Warning and Warnings and Precautions (5.2)], transient hepatic enzyme abnormalities, lupus-like syndromes, and the development of autoantibodies.

7 DRUG INTERACTIONS

7.1 Other Biological Products

The combination of AVSOLA with other biological products used to treat the same conditions as AVSOLA is not recommended [see Warnings and Precautions (5.10)].

An increased risk of serious infections was seen in clinical studies of other TNF blockers used in combination with anakinra or abatacept, with no added clinical benefit. Because of the nature of the adverse reactions seen with these combinations with TNF blocker therapy, similar toxicities may also result from the combination of anakinra or abatacept with other TNF blockers. Therefore, the combination of AVSOLA and anakinra or abatacept is not recommended [see Warnings and Precautions (5.10)].

The concomitant use of tocilizumab with biological DMARDs such as TNF antagonists, including AVSOLA, should be avoided because of the possibility of increased immunosuppression and increased risk of infection.

7.2 Methotrexate and Other Concomitant Medications

Specific drug interaction studies, including interactions with methotrexate (MTX), have not been conducted. The majority of patients in RA or CD clinical studies received one or more concomitant medications. In RA, concomitant medications besides MTX were non-steroidal anti-inflammatory agents (NSAIDs), folic acid, corticosteroids and/or narcotics. Concomitant CD medications were antibiotics, antivirals, corticosteroids, 6-MP/AZA and aminosalicylates. In PsA clinical trials, concomitant medications included MTX in approximately half of the patients as well as NSAIDs, folic acid and corticosteroids. Concomitant MTX use may decrease the incidence of anti-drug antibody production and increase infliximab product concentrations.

7.3 Immunosuppressants

Patients with CD who received immunosuppressants tended to experience fewer infusion reactions compared to patients on no immunosuppressants [see Adverse Reactions (6.1)]. Serum infliximab concentrations appeared to be unaffected by baseline use of medications for the treatment of CD including corticosteroids, antibiotics (metronidazole or ciprofloxacin) and aminosalicylates.

7.4 Cytochrome P450 Substrates

The formation of CYP450 enzymes may be suppressed by increased levels of cytokines (e.g., TNFα, IL-1, IL-6, IL-10, IFN) during chronic inflammation. Therefore, it is expected that for a molecule that antagonizes cytokine activity, such as infliximab products, the formation of CYP450 enzymes could be normalized. Upon initiation or discontinuation of AVSOLA in patients being treated with CYP450 substrates with a narrow therapeutic index, monitoring of the effect (e.g., warfarin) or drug concentration (e.g., cyclosporine or theophylline) is recommended and the individual dose of the drug product may be adjusted as needed.

7.5 Live Vaccines/Therapeutic Infectious Agents

It is recommended that live vaccines not be given concurrently with AVSOLA. It is also recommended that live vaccines not be given to infants after in utero exposure to infliximab products for at least 6 months following birth [see Warnings and Precautions (5.13)].

It is recommended that therapeutic infectious agents not be given concurrently with AVSOLA [see Warnings and Precautions (5.13)].

8 USE IN SPECIFIC POPULATIONS

8.1 Pregnancy

Risk Summary

Available observational studies in pregnant women exposed to infliximab products showed no increased risk of major malformations among live births as compared to those exposed to non-biologics. However, findings on other birth and maternal outcomes were not consistent across studies of different study design and conduct (see Data).

Monoclonal antibodies such as infliximab products are transferred across the placenta during the third trimester of pregnancy and may affect immune response in the in utero exposed infant (see Clinical Considerations). Because infliximab products do not cross-react with TNFα in species other than humans and chimpanzees, animal reproduction studies have not been conducted with infliximab products. In a developmental study conducted in mice using an analogous antibody, no evidence of maternal toxicity or fetal harm was observed (see Data).

All pregnancies have a background risk of birth defect, loss, or other adverse outcomes.

The estimated background risk of major birth defects and miscarriage for the indicated populations is unknown. In the U.S. general population, the estimated background risk of major birth defects and miscarriage in clinically recognized pregnancies is 2-4% and 15-20%, respectively.

Clinical Considerations

Disease-Associated Maternal and/or Embryo/Fetal Risk

Published data suggest that there is an increased risk of adverse pregnancy outcomes in women with inflammatory bowel disease or rheumatoid arthritis associated with increased disease activity. Adverse pregnancy outcomes include preterm delivery (before 37 weeks of gestation), low birth weight (less than 2.5 kg) and small for gestational age at birth.

Fetal/Neonatal Adverse Reactions

As with other IgG antibodies, infliximab products cross the placenta. Infliximab products have been detected in the serum of infants up to 6 months following birth. Consequently, these infants may be at increased risk of infection, including disseminated infection which can become fatal. At least a six-month waiting period following birth is recommended before the administration of live vaccines (e.g., BCG vaccine or other live vaccines, such as the rotavirus vaccine) to these infants [see Warnings and Precautions (5.13)]. Cases of agranulocytosis in infants exposed in utero have also been reported [see Adverse Reactions (6.3)].

Data

Human Data

Two prospective cohort studies were conducted assessing birth outcomes as well as the health status of infants up to the age of one year in women exposed to infliximab compared to non-biologic comparators including methotrexate, azathioprine, 6-mercaptopurine and systemic corticosteroids used for the treatment of similar diseases. The first study was conducted in an IBD pregnancy registry in the United States and assessed pregnancy outcomes in 294 women with inflammatory bowel disease exposed to infliximab during pregnancy compared with 515 women on a non-biologic treatment. Infliximab exposure was not associated with increased rates of major congenital malformations, miscarriage/stillbirth, infants of low birth weight, small for gestational age, or infection in the first year of life. The second study among IBD and non-IBD patients in Sweden, Finland, and Denmark compared 97, 7, and 166 women exposed to infliximab to 2,693, 2,499 and 1,268 women on non-biologic systemic therapy, respectively. In this study, comparing pooled data across the three countries, exposure to infliximab was not associated with increased rates of congenital anomalies or infant death. Infliximab in combination with immunosuppressants (mainly systemic corticosteroids and azathioprine) was associated with increased rates of preterm birth, small for gestational age, low birth weight, and infant hospitalization for infection compared with non-biologic systemic treatment. Although the study did not show any associations with infliximab monotherapy, the analyses could have been underpowered to detect an association.

There were additional methodological limitations with these studies that may account for the study findings in both studies: the concomitant use of other medications or treatments was not controlled and disease severity was not assessed; in the U.S. study, patient reported outcomes were collected without clinical validation. These methodological limitations hinder interpretation of the study results.

Animal Data

Because infliximab products do not cross-react with TNFα in species other than humans and chimpanzees, animal reproduction studies have not been conducted with infliximab products. An embryofetal development study was conducted in pregnant mice using cV1q anti-mouse TNFα, an analogous antibody that selectively inhibits the functional activity of mouse TNFα. This antibody, administered in mice, during the period of organogenesis on gestation days (GDs) 6 and 12, at IV doses up to 40 mg/kg produced no evidence of maternal toxicity, fetal mortality, or structural abnormalities. Doses of 10 to 15 mg/kg in pharmacodynamic animal models with the anti-TNF analogous antibody produced maximal pharmacologic effectiveness. Analyses of fetal samples on GD 14 indicated placental transfer of the antibody and exposure of the fetuses during organogenesis. In a peri- and post-natal development study in mice, no maternal toxicity or adverse developmental effects in offspring were observed when dams were administered IV doses of 10 or 40 mg/kg of the analogous antibody on GDs 6, 12 and 18 and lactation days 3, 9 and 15.

8.2 Lactation

Risk Summary

Published literature show that infliximab is present at low levels in human milk. Systemic exposure in a breastfed infant is expected to be low because infliximab products are largely degraded in the gastrointestinal tract. A U.S. multi-center study of 168 women treated with infliximab for inflammatory bowel disease (breast milk samples obtained, n=29) showed that infants exposed to infliximab through breast milk had no increase in rates of infections and developed normally. There are no data on the effects of infliximab products on milk production. The developmental and health benefits of breastfeeding should be considered along with the mother's clinical need for AVSOLA and any potential adverse effects on the breastfed child from AVSOLA or from the underlying maternal condition.

8.4 Pediatric Use

The safety and effectiveness of AVSOLA have been established in pediatric patients 6 to 17 years of age for induction and maintenance treatment of CD and UC [see Dosage and Administration (2.2, 2.4) and Adverse Reactions (6.1)]. However, the safety and effectiveness of AVSOLA in pediatric patients <6 years of age with CD or UC have not been established. The safety and effectiveness of AVSOLA in the treatment of pediatric patients with Ps and juvenile rheumatoid arthritis (JRA) have not been established.

Pediatric Crohn's Disease

The safety and effectiveness of AVSOLA have been established for reducing signs and symptoms and inducing and maintaining clinical remission in pediatric patients 6 years of age and older with moderately to severely active CD who have had an inadequate response to conventional therapy. The use of AVSOLA for this indication is supported by evidence from a randomized, open-label pediatric CD study of infliximab in 112 pediatric patients aged 6 years and older [see Clinical Studies (14.2)].

Infliximab has been studied only in combination with conventional immunosuppressive therapy in pediatric CD. The longer term (greater than 1 year) safety and effectiveness of infliximab products in pediatric CD patients have not been established in clinical trials.

Postmarketing cases of HSTCL have been reported in pediatric patients treated with TNF blockers including infliximab products. Due to the risk of HSTCL, a careful risk-benefit assessment should be made when AVSOLA is used in combination with other immunosuppressants in pediatric CD patients [see Boxed Warning and Warnings and Precautions (5.2)].

Pediatric Ulcerative Colitis

The safety and effectiveness of AVSOLA for reducing signs and symptoms and inducing and maintaining clinical remission in pediatric patients aged 6 years and older with moderately to severely active UC who have had an inadequate response to conventional therapy have been established. The use of AVSOLA for this indication is supported by evidence from adequate and well-controlled studies of infliximab in adults with additional safety and pharmacokinetic data from an open-label pediatric UC study in 60 pediatric patients aged 6 years and older [see Dosage and Administration (2.4), Adverse Reactions (6.1), and Clinical Studies (14.4)]. The effectiveness of infliximab in inducing and maintaining mucosal healing in pediatric UC was not established. Although 41 patients had a Mayo endoscopy subscore of 0 or 1 at the Week 8 endoscopy, the induction phase was open-label and lacked a control group. Only 9 patients had an optional endoscopy at Week 54. Approximately half of the patients were on concomitant immunomodulators (AZA, 6-MP, MTX) at study start.

Due to the risk of HSTCL, a careful risk-benefit assessment should be made when AVSOLA is used in combination with other immunosuppressants in pediatric UC patients [see Boxed Warning and Warnings and Precautions (5.2)].

The longer term (greater than 1 year) safety and effectiveness of infliximab products in pediatric UC patients have not been established in clinical trials.

Juvenile Rheumatoid Arthritis (JRA)

The safety and effectiveness of AVSOLA in the treatment of pediatric patients with juvenile rheumatoid arthritis (JRA) have not been established.

The safety and efficacy of AVSOLA in patients with JRA is based on the evaluation of infliximab in a multicenter, randomized, placebo-controlled, double-blind study for 14 weeks, followed by a double-blind, all-active treatment extension, for a maximum of 44 weeks. Patients with active JRA between the ages of 4 and 17 years who had been treated with MTX for at least 3 months were enrolled. Concurrent use of folic acid, oral corticosteroids (≤0.2 mg/kg/day of prednisone or equivalent), NSAIDs, and/or disease-modifying antirheumatic drugs (DMARDs) was permitted.

Doses of 3 mg/kg infliximab or placebo were administered intravenously at Weeks 0, 2 and 6. Patients randomized to placebo crossed over to receive 6 mg/kg infliximab at Weeks 14, 16, and 20, and then every 8 weeks through Week 44. Patients who completed the study continued to receive open-label treatment with infliximab for up to 2 years in a companion extension study.

The study failed to establish the efficacy of infliximab in the treatment of JRA. Key observations in the study included a high placebo response rate and a higher rate of immunogenicity than what has been observed in adults. Additionally, a higher rate of clearance of infliximab was observed than had been observed in adults.

Population pharmacokinetic analysis showed that in pediatric patients with JRA with a body weight of up to 35 kg receiving 6 mg/kg infliximab and pediatric patients with JRA with body weight greater than 35 kg up to adult body weight receiving 3 mg/kg infliximab, the steady state area under the concentration curve (AUCss) was similar to that observed in adults receiving 3 mg/kg of infliximab.

A total of 60 patients with JRA were treated with doses of 3 mg/kg and 57 patients were treated with doses of 6 mg/kg. The proportion of patients with infusion reactions who received 3 mg/kg infliximab was 35% (21/60) over 52 weeks compared with 18% (10/57) in patients who received 6 mg/kg over 38 weeks. The most common infusion reactions reported were vomiting, fever, headache, and hypotension. In the 3 mg/kg infliximab group, 4 patients had a serious infusion reaction and 3 patients reported a possible anaphylactic reaction (2 of which were among the serious infusion reactions). In the 6 mg/kg infliximab group, 2 patients had a serious infusion reaction, 1 of whom had a possible anaphylactic reaction. Two of the 6 patients who experienced serious infusion reactions received infliximab by rapid infusion (duration of less than 2 hours). Antibodies to infliximab developed in 38% (20/53) of patients who received 3 mg/kg infliximab compared with 12% (6/49) of patients who received 6 mg/kg.

A total of 68% (41/60) of patients who received 3 mg/kg infliximab in combination with MTX experienced an infection over 52 weeks compared with 65% (37/57) of patients who received 6 mg/kg infliximab in combination with MTX over 38 weeks. The most commonly reported infections were upper respiratory tract infection and pharyngitis, and the most commonly reported serious infection was pneumonia. Other notable infections included primary varicella infection in 1 patient and herpes zoster in 1 patient.

8.5 Geriatric Use

Of the total number of infliximab-treated patients in RA and Ps clinical studies, 256 (9.6%) were 65 years old and over, while 17 (0.6%) were 75 years old and over. In these trials, no overall differences in safety or effectiveness were observed between geriatric patients (patients ≥65 years old) and younger adult patients (patients 18 to 65 years old). However, the incidence of serious adverse reactions in geriatric patients was higher in both infliximab and control groups compared to younger adult patients.

Of the total number of infliximab-treated patients in CD, UC, AS, and PsA clinical studies, 76 (3.2%) were 65 years old and over, while 9 (0.4%) were 75 years old and over. In CD, UC, AS and PsA studies, there were insufficient numbers of geriatric patients to determine whether they respond differently from younger adults.

The incidence of serious infections in infliximab-treated geriatric patients was greater than in infliximab-treated younger adult patients; therefore close monitoring of geriatric patients for the development of serious infections is recommended [see Warnings and Precautions (5.1) and Adverse Reactions (6.1)].

10 OVERDOSAGE

Single doses up to 20 mg/kg have been administered without any direct toxic effect. In case of overdosage, it is recommended that the patient be monitored for any signs or symptoms of adverse reactions or effects [see Warnings and Precautions (5)] and appropriate symptomatic treatment instituted immediately.

11 DESCRIPTION

Infliximab-axxq, a tumor necrosis factor (TNF) blocker, is a chimeric IgG1κ monoclonal antibody (composed of human constant and murine variable regions). It has a molecular weight of approximately 149.1 kilodaltons. Infliximab-axxq is produced in a recombinant Chinese Hamster Ovary (CHO) cell line.

AVSOLA (infliximab-axxq) for injection is supplied as a sterile, preservative-free, white to slightly yellow, lyophilized powder for intravenous infusion after reconstitution and dilution. Following reconstitution with 10 mL of Sterile Water for Injection, USP, the final concentration is 10 mg/mL and the resulting pH is approximately 7.2. Each single-dose vial contains 100 mg infliximab-axxq, dibasic sodium phosphate, anhydrous (4.9 mg), monobasic sodium phosphate, monohydrate (2.2 mg), polysorbate 80 (0.5 mg), and sucrose (500 mg).

12 CLINICAL PHARMACOLOGY

12.1 Mechanism of Action

Infliximab products neutralize the biological activity of TNFα by binding with high affinity to the soluble and transmembrane forms of TNFα and inhibit binding of TNFα with its receptors. Infliximab products do not neutralize TNFβ (lymphotoxin-α), a related cytokine that utilizes the same receptors as TNFα. Biological activities attributed to TNFα include: induction of pro-inflammatory cytokines such as interleukins (IL) 1 and 6, enhancement of leukocyte migration by increasing endothelial layer permeability and expression of adhesion molecules by endothelial cells and leukocytes, activation of neutrophil and eosinophil functional activity, induction of acute phase reactants and other liver proteins, as well as tissue degrading enzymes produced by synoviocytes and/or chondrocytes. Cells expressing transmembrane TNFα bound by infliximab products can be lysed in vitro or in vivo. Infliximab products inhibit the functional activity of TNFα in a wide variety of in vitro bioassays utilizing human fibroblasts, endothelial cells, neutrophils, B and T-lymphocytes and epithelial cells. The relationship of these biological response markers to the mechanism(s) by which infliximab products exert their clinical effects is unknown. Anti-TNFα antibodies reduce disease activity in the cotton-top tamarin colitis model, and decrease synovitis and joint erosions in a murine model of collagen-induced arthritis. Infliximab products prevent disease in transgenic mice that develop polyarthritis as a result of constitutive expression of human TNFα, and when administered after disease onset, allow eroded joints to heal.

12.2 Pharmacodynamics

Elevated concentrations of TNFα have been found in involved tissues and fluids of patients with RA, CD, UC, AS, PsA and Ps. In RA, treatment with infliximab products reduced infiltration of inflammatory cells into inflamed areas of the joint as well as expression of molecules mediating cellular adhesion [E-selectin, intercellular adhesion molecule-1 (ICAM-1) and vascular cell adhesion molecule-1 (VCAM-1)], chemoattraction [IL-8 and monocyte chemotactic protein (MCP-1)] and tissue degradation [matrix metalloproteinase (MMP) 1 and 3]. In CD, treatment with infliximab products reduced infiltration of inflammatory cells and TNFα production in inflamed areas of the intestine, and reduced the proportion of mononuclear cells from the lamina propria able to express TNFα and interferon. After treatment with infliximab products, patients with RA or CD exhibited decreased levels of serum IL-6 and C-reactive protein (CRP) compared to baseline. Peripheral blood lymphocytes from patients treated with infliximab products showed no significant decrease in number or in proliferative responses to in vitro mitogenic stimulation when compared to cells from untreated patients. In PsA, treatment with infliximab products resulted in a reduction in the number of T-cells and blood vessels in the synovium and psoriatic skin lesions as well as a reduction of macrophages in the synovium. In Ps, infliximab products treatment may reduce the epidermal thickness and infiltration of inflammatory cells. The relationship between these pharmacodynamic activities and the mechanism(s) by which infliximab products exert their clinical effects is unknown.

12.3 Pharmacokinetics

In adults, single intravenous (IV) infusions of 3 mg/kg to 20 mg/kg (two times the maximum recommended dose for any indication) of infliximab showed a linear relationship between the dose administered and the maximum serum concentration. The volume of distribution at steady state was independent of dose and indicated that infliximab was distributed primarily within the vascular compartment. Pharmacokinetic results for single doses of 3 mg/kg to 10 mg/kg in RA, 5 mg/kg in CD, and 3 mg/kg to 5 mg/kg in Ps indicate that the median terminal half-life of infliximab is 7.7 to 9.5 days.

Following an initial dose of infliximab, repeated infusions at 2 and 6 weeks resulted in predictable concentration-time profiles following each treatment. No systemic accumulation of infliximab occurred upon continued repeated treatment with 3 mg/kg or 10 mg/kg at 4- or 8-week intervals. Development of antibodies to infliximab increased infliximab clearance. At 8 weeks after a maintenance dose of 3 to 10 mg/kg of infliximab, median infliximab serum concentrations ranged from approximately 0.5 to 6 mcg/mL; however, infliximab concentrations were not detectable (<0.1 mcg/mL) in patients who became positive for antibodies to infliximab. No major differences in clearance or volume of distribution were observed in patient subgroups defined by age, weight, or gender. It is not known if there are differences in clearance or volume of distribution in patients with marked impairment of hepatic or renal function.

Infliximab pharmacokinetic characteristics (including peak and trough concentrations and terminal half-life) were similar in pediatric (aged 6 to 17 years) and adult patients with CD or UC following the administration of 5 mg/kg infliximab.

13 NONCLINICAL TOXICOLOGY

13.1 Carcinogenesis, Mutagenesis, Impairment of Fertility

A 6-month study in CD-1 mice was conducted to assess the tumorigenic potential of cV1q anti-mouse TNFα, an analogous antibody. No evidence of tumorigenicity was observed in mice that received intravenous doses of 10 mg/kg or 40 mg/kg cV1q given weekly. The relevance of this study for human risk is unknown. No impairment of fertility or reproductive performance indices were observed in male or female mice that received cV1q, an analogous mouse antibody, at intravenous doses up to 40 mg/kg given weekly.

14 CLINICAL STUDIES

14.1 Adult Crohn's Disease

Active Crohn's Disease in Adults

The safety and efficacy of single and multiple doses of infliximab were assessed in 2 randomized, double-blind, placebo-controlled clinical studies in 653 adult patients with moderate to severely active CD [Crohn's Disease Activity Index (CDAI) ≥220 and ≤400] with an inadequate response to prior conventional therapies. Concomitant stable doses of aminosalicylates, corticosteroids and/or immunomodulatory agents were permitted and 92% of patients continued to receive at least one of these medications.

In the single-dose trial of 108 adult patients, 16% (4/25) of placebo patients achieved a clinical response (decrease in CDAI ≥70 points) at Week 4 vs. 81% (22/27) of patients receiving 5 mg/kg infliximab (p<0.001, two-sided, Fisher's Exact test). Additionally, 4% (1/25) of placebo patients and 48% (13/27) of patients receiving 5 mg/kg infliximab achieved clinical remission (CDAI<150) at Week 4.

In a multidose trial (ACCENT I [Study Crohn's I]), 545 adult patients received 5 mg/kg at Week 0 and were then randomized to one of three treatment groups; the placebo maintenance group received placebo at Weeks 2 and 6, and then every 8 weeks; the 5 mg/kg maintenance group received 5 mg/kg at Weeks 2 and 6, and then every 8 weeks; and the 10 mg/kg maintenance group received 5 mg/kg at Weeks 2 and 6, and then 10 mg/kg every 8 weeks. Patients in response at Week 2 were randomized and analyzed separately from those not in response at Week 2. Corticosteroid taper was permitted after Week 6.

At Week 2, 57% (311/545) of patients were in clinical response. At Week 30, a significantly greater proportion of these patients in the 5 mg/kg and 10 mg/kg maintenance groups achieved clinical remission compared to patients in the placebo maintenance group (Table 3).

Additionally, a significantly greater proportion of patients in the 5 mg/kg and 10 mg/kg infliximab maintenance groups were in clinical remission and were able to discontinue corticosteroid use compared to patients in the placebo maintenance group at Week 54 (Table 3).

Table 3: Clinical Remission and Steroid Withdrawal in Adult Patients with CD (Study Crohn's I)
 | Single 5 mg/kg Dose [Infliximab at Week 0] | Three-Dose Induction [Infliximab 5 mg/kg administered at Weeks 0, 2 and 6]
 | Placebo Maintenance | Infliximab Maintenance q8 wks
 |  | 5 mg/kg | 10 mg/kg
Week 30 | 25/102 | 41/104 | 48/105
Clinical remission | 25% | 39% | 46%
P-value [P-values represent pairwise comparisons to placebo] |  | 0.022 | 0.001
Week 54 | 6/54 | 14/56 | 18/53
Patients in remission able to discontinue corticosteroid use [Of those receiving corticosteroids at baseline] | 11% | 25% | 34%
P-value |  | 0.059 | 0.005

Patients in the infliximab maintenance groups (5 mg/kg and 10 mg/kg) had a longer time to loss of response than patients in the placebo maintenance group (Figure 1). At Weeks 30 and 54, significant improvement from baseline was seen among the 5 mg/kg and 10 mg/kg infliximab-treated groups compared to the placebo group in the disease-specific inflammatory bowel disease questionnaire (IBDQ), particularly the bowel and systemic components, and in the physical component summary score of the general health-related quality of life questionnaire SF-36.

Figure 1: Kaplan-Meier Estimate of the Proportion of Adults with CD Who Had Not Lost Response through Week 54 (Study Crohn's I)

In a subset of 78 patients who had mucosal ulceration at baseline and who participated in an endoscopic substudy, 13 of 43 patients in the infliximab maintenance group had endoscopic evidence of mucosal healing compared to 1 of 28 patients in the placebo group at Week 10. Of the infliximab-treated patients showing mucosal healing at Week 10, 9 of 12 patients also showed mucosal healing at Week 54.

Patients who achieved a response and subsequently lost response were eligible to receive infliximab on an episodic basis at a dose that was 5 mg/kg higher than the dose to which they were randomized. The majority of such patients responded to the higher dose. Among patients who were not in response at Week 2, 59% (92/157) of infliximab maintenance patients responded by Week 14 compared to 51% (39/77) of placebo maintenance patients. Among patients who did not respond by Week 14, additional therapy did not result in significantly more responses [see Dosage and Administration (2)].

Fistulizing Crohn's Disease in Adults

The safety and efficacy of infliximab were assessed in 2 randomized, double-blind, placebo-controlled studies in adult patients with fistulizing CD with fistula(s) that were of at least 3 months duration. Concurrent use of stable doses of corticosteroids, 5-aminosalicylates, antibiotics, MTX, 6-mercaptopurine (6-MP) and/or azathioprine (AZA) was permitted.

In the first trial, 94 adult patients received 3 doses of either placebo or infliximab at Weeks 0, 2 and 6. Fistula response (≥50% reduction in number of enterocutaneous fistulas draining upon gentle compression on at least 2 consecutive visits without an increase in medication or surgery for CD) was seen in 68% (21/31) of patients in the 5 mg/kg infliximab group (P=0.002) and 56% (18/32) of patients in the 10 mg/kg infliximab group (P=0.021) vs. 26% (8/31) of patients in the placebo arm. The median time to onset of response and median duration of response in infliximab-treated patients was 2 and 12 weeks, respectively. Closure of all fistulas was achieved in 52% of infliximab-treated patients compared with 13% of placebo-treated patients (P<0.001).

In the second trial (ACCENT II [Study Crohn's II]), adult patients who were enrolled had to have at least 1 draining enterocutaneous (perianal, abdominal) fistula. All patients received 5 mg/kg infliximab at Weeks 0, 2 and 6. Patients were randomized to placebo or 5 mg/kg infliximab maintenance at Week 14. Patients received maintenance doses at Week 14 and then every 8 weeks through Week 46. Patients who were in fistula response (fistula response was defined the same as in the first trial) at both Weeks 10 and 14 were randomized separately from those not in response. The primary endpoint was time from randomization to loss of response among those patients who were in fistula response.

Among the randomized patients (273 of the 296 initially enrolled), 87% had perianal fistulas and 14% had abdominal fistulas. Eight percent also had rectovaginal fistulas. Greater than 90% of the patients had received previous immunosuppressive and antibiotic therapy.

At Week 14, 65% (177/273) of patients were in fistula response. Patients randomized to infliximab maintenance had a longer time to loss of fistula response compared to the placebo maintenance group (Figure 2). At Week 54, 38% (33/87) of infliximab-treated patients had no draining fistulas compared with 22% (20/90) of placebo-treated patients (P=0.02). Compared to placebo maintenance, patients on infliximab maintenance had a trend toward fewer hospitalizations.

Figure 2: Life Table Estimates of the Proportion of Adult CD Patients Who Had Not Lost Fistula Response through Week 54 (Study Crohn's II)

Patients who achieved a fistula response and subsequently lost response were eligible to receive infliximab maintenance therapy at a dose that was 5 mg/kg higher than the dose to which they were randomized. Of the placebo maintenance patients, 66% (25/38) responded to 5 mg/kg infliximab, and 57% (12/21) of infliximab maintenance patients responded to 10 mg/kg.

Patients who had not achieved a response by Week 14 were unlikely to respond to additional doses of infliximab.

Similar proportions of patients in either group developed new fistulas (17% overall) and similar numbers developed abscesses (15% overall).

14.2 Pediatric Crohn's Disease

The safety and efficacy of infliximab were assessed in a randomized, open-label study (Study Peds Crohn's) in 112 pediatric patients aged 6 to 17 years old with moderately to severely active CD and an inadequate response to conventional therapies. The median age was 13 years and the median Pediatric Crohn's Disease Activity Index (PCDAI) was 40 (on a scale of 0 to 100). All patients were required to be on a stable dose of 6-MP, AZA, or MTX; 35% were also receiving corticosteroids at baseline.

All patients received induction dosing of 5 mg/kg infliximab at Weeks 0, 2 and 6. At Week 10, 103 patients were randomized to a maintenance regimen of 5 mg/kg of infliximab given either every 8 weeks or every 12 weeks.

At Week 10, 88% of patients were in clinical response (defined as a decrease from baseline in the PCDAI score of ≥15 points and total PCDAI score of ≤30 points), and 59% were in clinical remission (defined as PCDAI score of ≤10 points). The proportion of pediatric patients achieving clinical response at Week 10 compared favorably with the proportion of adults achieving a clinical response in Study Crohn's I. The study definition of clinical response in Study Peds Crohn's was based on the PCDAI score, whereas the CDAI score was used in the adult Study Crohn's I.

At both Week 30 and Week 54, the proportion of patients in clinical response was greater in the every 8-week treatment group than in the every 12-week treatment group (73% vs. 47% at Week 30, and 64% vs. 33% at Week 54). At both Week 30 and Week 54, the proportion of patients in clinical remission was also greater in the every 8-week treatment group than in the every 12-week treatment group (60% vs. 35% at Week 30, and 56% vs. 24% at Week 54), (Table 4).

For patients in Study Peds Crohn's receiving corticosteroids at baseline, the proportion of patients able to discontinue corticosteroids while in remission at Week 30 was 46% for the every 8-week maintenance group and 33% for the every 12-week maintenance group. At Week 54, the proportion of patients able to discontinue corticosteroids while in remission was 46% for the every 8-week maintenance group and 17% for the every 12-week maintenance group.

Table 4: Response and Remission in Study Peds Crohn's
 | 5 mg/kg Infliximab
 | Every 8-Week | Every 12-Week
 | Treatment Group | Treatment Group
Patients randomized | 52 | 51
Clinical Response [Defined as a decrease from baseline in the PCDAI score of ≥15 points and total score of ≤30 points.]
Week 30 | 73% [P-value <0.01] | 47%
Week 54 | 64% | 33%
Clinical Remission [Defined as a PCDAI score of ≤10 points.]
Week 30 | 60% [P-value <0.05] | 35%
Week 54 | 56% | 24%

14.3 Adult Ulcerative Colitis

The safety and efficacy of infliximab were assessed in 2 randomized, double-blind, placebo-controlled clinical studies in 728 adult patients with moderately to severely active UC (Mayo score 6 to 12 [of possible range 0 to 12], Endoscopy subscore ≥2) with an inadequate response to conventional oral therapies (Studies UC I and UC II). Concomitant treatment with stable doses of aminosalicylates, corticosteroids and/or immunomodulatory agents was permitted. Corticosteroid taper was permitted after Week 8. Patients were randomized at week 0 to receive either placebo, 5 mg/kg infliximab or 10 mg/kg infliximab at Weeks 0, 2, 6, and every 8 weeks thereafter through Week 46 in Study UC I, and at Weeks 0, 2, 6, and every 8 weeks thereafter through Week 22 in Study UC II. In Study UC II, patients were allowed to continue blinded therapy to Week 46 at the investigator's discretion.

Adult patients in Study UC I had failed to respond or were intolerant to oral corticosteroids, 6-MP, or AZA. Adult patients in Study UC II had failed to respond or were intolerant to the above treatments and/or aminosalicylates. Similar proportions of patients in Studies UC I and UC II were receiving corticosteroids (61% and 51%, respectively), 6-MP/AZA (49% and 43%) and aminosalicylates (70% and 75%) at baseline. More patients in Study UC II than UC I were taking solely aminosalicylates for UC (26% vs. 11%, respectively). Clinical response was defined as a decrease from baseline in the Mayo score by ≥30% and ≥3 points, accompanied by a decrease in the rectal bleeding subscore of ≥1 or a rectal bleeding subscore of 0 or 1.

Clinical Response, Clinical Remission, and Mucosal Healing

In both Study UC I and Study UC II, greater percentages of patients in both infliximab groups achieved clinical response, clinical remission and mucosal healing than in the placebo group. Each of these effects was maintained through the end of each trial (Week 54 in Study UC I, and Week 30 in Study UC II). In addition, a greater proportion of patients in infliximab groups demonstrated sustained response and sustained remission than in the placebo groups (Table 5).

Of patients on corticosteroids at baseline, greater proportions of adult patients in the infliximab treatment groups were in clinical remission and able to discontinue corticosteroids at Week 30 compared with the patients in the placebo treatment groups (22% in infliximab treatment groups vs. 10% in placebo group in Study UC I; 23% in infliximab treatment groups vs. 3% in placebo group in Study UC II). In Study UC I, this effect was maintained through Week 54 (21% in infliximab treatment groups vs. 9% in placebo group). The infliximab-associated response was generally similar in the 5 mg/kg and 10 mg/kg dose groups.

Table 5: Response, Remission and Mucosal Healing in Adult UC Studies (Studies UC I and UC II)
 | Study UC I |  |  | Study UC II
 | Placebo | 5 mg/kg Infliximab | 10 mg/kg Infliximab | Placebo | 5 mg/kg Infliximab | 10 mg/kg Infliximab
Patients randomized | 121 | 121 | 122 | 123 | 121 | 120
Clinical Response [Defined as a decrease from baseline in the Mayo score by ≥30% and ≥3 points, accompanied by a decrease in the rectal bleeding subscore of ≥1 or a rectal bleeding subscore of 0 or 1 (The Mayo score consists of the sum of four subscores: stool frequency, rectal bleeding, physician's global assessment and endoscopy findings).] , [Patients who had a prohibited change in medication, had an ostomy or colectomy, or discontinued study infusions due to lack of efficacy are considered to not be in clinical response, clinical remission or mucosal healing from the time of the event onward.]
Week 8 | 37% | 69% [P<0.001,] | 62% | 29% | 65% | 69%
Week 30 | 30% | 52% | 51% [P<0.01] | 26% | 47% | 60%
Week 54 | 20% | 45% | 44% | NA | NA | NA
Sustained Response
(Clinical response at both Weeks 8 and 30) | 23% | 49% | 46% | 15% | 41% | 53%
(Clinical response at Weeks 8, 30, and 54) | 14% | 39% | 37% | NA | NA | NA
Clinical Remission [Defined as a Mayo score ≤2 points, no individual subscore >1.] ,
Week 8 | 15% | 39% | 32% | 6% | 34% | 28%
Week 30 | 16% | 34% | 37% | 11% | 26% | 36%
Week 54 | 17% | 35% | 34% | NA | NA | NA
Sustained Remission
(Clinical remission at both Weeks 8 and 30) | 8% | 23% | 26% | 2% | 15% | 23%
(Clinical remission at Weeks 8, 30 and 54) | 7% | 20% | 20% | NA | NA | NA
Mucosal Healing [Defined as a 0 or 1 on the endoscopy subscore of the Mayo score.] ,
Week 8 | 34% | 62% | 59% | 31% | 60% | 62%
Week 30 | 25% | 50% | 49% | 30% | 46% | 57%
Week 54 | 18% | 45% | 47% | NA | NA | NA

The improvement with infliximab was consistent across all Mayo subscores through Week 54 (Study UC I shown in Table 6; Study UC II through Week 30 was similar).

Table 6: Proportion of Adult UC Patients in Study UC I with Mayo Subscores Indicating Inactive or Mild Disease through Week 54
 | Study UC I
 |  | Infliximab
 | Placebo | 5 mg/kg | 10 mg/kg
 | (n = 121) | (n = 121) | (n = 122)
Stool frequency
Baseline | 17% | 17% | 10%
Week 8 | 35% | 60% | 58%
Week 30 | 35% | 51% | 53%
Week 54 | 31% | 52% | 51%
Rectal bleeding
Baseline | 54% | 40% | 48%
Week 8 | 74% | 86% | 80%
Week 30 | 65% | 74% | 71%
Week 54 | 62% | 69% | 67%
Physician's Global Assessment
Baseline | 4% | 6% | 3%
Week 8 | 44% | 74% | 64%
Week 30 | 36% | 57% | 55%
Week 54 | 26% | 53% | 53%
Endoscopy findings
Baseline | 0% | 0% | 0%
Week 8 | 34% | 62% | 59%
Week 30 | 26% | 51% | 52%
Week 54 | 21% | 50% | 51%

14.4 Pediatric Ulcerative Colitis

The safety and effectiveness of infliximab products for reducing signs and symptoms and inducing and maintaining clinical remission in pediatric patients aged 6 years and older with moderately to severely active UC who have had an inadequate response to conventional therapy are supported by evidence from adequate and well-controlled studies of infliximab in adults. Additional safety and pharmacokinetic data were collected in an open-label pediatric UC trial in 60 pediatric patients aged 6 through 17 years (median age 14.5 years) with moderately to severely active UC (Mayo score of 6 to 12; Endoscopic subscore ≥2) and an inadequate response to conventional therapies. At baseline, the median Mayo score was 8, 53% of patients were receiving immunomodulator therapy (6-MP/AZA/MTX), and 62% of patients were receiving corticosteroids (median dose 0.5 mg/kg/day in prednisone equivalents). Discontinuation of immunomodulators and corticosteroid taper were permitted after Week 0.

All patients received induction dosing of 5 mg/kg infliximab at Weeks 0, 2 and 6. Patients who did not respond to infliximab at Week 8 received no further infliximab and returned for safety follow-up. At Week 8, 45 patients were randomized to a maintenance regimen of 5 mg/kg infliximab given either every 8 weeks through Week 46 or every 12 weeks through Week 42. Patients were allowed to change to a higher dose and/or more frequent administration schedule if they experienced loss of response.

Clinical response at Week 8 was defined as a decrease from baseline in the Mayo score by ≥30% and ≥3 points, including a decrease in the rectal bleeding subscore by ≥1 points or achievement of a rectal bleeding subscore of 0 or 1.

Clinical remission at Week 8 was measured by the Mayo score, defined as a Mayo score of ≤2 points with no individual subscore >1. Clinical remission was also assessed at Week 8 and Week 54 using the Pediatric Ulcerative Colitis Activity Index (PUCAI)^1 score and was defined by a PUCAI score of <10 points.

Endoscopies were performed at baseline and at Week 8. A Mayo endoscopy subscore of 0 indicated normal or inactive disease and a subscore of 1 indicated mild disease (erythema, decreased vascular pattern, or mild friability).

Of the 60 patients treated, 44 were in clinical response at Week 8. Of 32 patients taking concomitant immunomodulators at baseline, 23 achieved clinical response at Week 8, compared to 21 of 28 of those not taking concomitant immunomodulators at baseline. At Week 8, 24 of 60 patients were in clinical remission as measured by the Mayo score and 17 of 51 patients were in remission as measured by the PUCAI score.

At Week 54, 8 of 21 patients in the every 8-week maintenance group and 4 of 22 patients in the every 12-week maintenance group achieved remission as measured by the PUCAI score.

During maintenance phase, 23 of 45 randomized patients (9 in the every 8-week group and 14 in the every 12-week group) required an increase in their dose and/or increase in frequency of infliximab administration due to loss of response. Nine of the 23 patients who required a change in dose had achieved remission at Week 54. Seven of those patients received the 10 mg/kg every 8-week dosing.

14.5 Rheumatoid Arthritis

The safety and efficacy of infliximab in adult patients with RA were assessed in 2 multicenter, randomized, double-blind, pivotal trials: ATTRACT (Study RA I) and ASPIRE (Study RA II). Concurrent use of stable doses of folic acid, oral corticosteroids (≤10 mg/day) and/or non-steroidal anti-inflammatory drugs (NSAIDs) was permitted.

Study RA I was a placebo-controlled study of 428 patients with active RA despite treatment with MTX. Patients enrolled had a median age of 54 years, median disease duration of 8.4 years, median swollen and tender joint count of 20 and 31 respectively, and were on a median dose of 15 mg/wk of MTX. Patients received either placebo + MTX or one of 4 doses/schedules of infliximab + MTX: 3 mg/kg or 10 mg/kg of infliximab by IV infusion at Weeks 0, 2 and 6 followed by additional infusions every 4 or 8 weeks in combination with MTX.

Study RA II was a placebo-controlled study of 3 active treatment arms in 1004 MTX naive patients of 3 or fewer years duration active RA. Patients enrolled had a median age of 51 years with a median disease duration of 0.6 years, median swollen and tender joint count of 19 and 31, respectively, and >80% of patients had baseline joint erosions. At randomization, all patients received MTX (optimized to 20 mg/wk by Week 8) and either placebo, 3 mg/kg or 6 mg/kg infliximab at Weeks 0, 2 and 6 and every 8 weeks thereafter.

Data on use of infliximab products without concurrent MTX are limited [see Adverse Reactions (6.1)].

Clinical Response

In Study RA I, all doses/schedules of infliximab + MTX resulted in improvement in signs and symptoms as measured by the American College of Rheumatology response criteria (ACR 20) with a higher percentage of patients achieving an ACR 20, 50 and 70 compared to placebo + MTX (Table 7). This improvement was observed at Week 2 and maintained through Week 102. Greater effects on each component of the ACR 20 were observed in all patients treated with infliximab + MTX compared to placebo + MTX (Table 8). More patients treated with infliximab reached a major clinical response than placebo-treated patients (Table 7). In Study RA II, after 54 weeks of treatment, both doses of infliximab + MTX resulted in statistically significantly greater response in signs and symptoms compared to MTX alone as measured by the proportion of patients achieving ACR 20, 50 and 70 responses (Table 7). More patients treated with infliximab reached a major clinical response than placebo-treated patients (Table 7).

Table 7: ACR Response (percent of patients) in Adult RA Patients (Studies RA I and RA II)
 | Study RA I |  |  |  |  | Study RA II
 |  | Infliximab + MTX |  |  |  |  | Infliximab + MTX
 |  | 3 mg/kg |  | 10 mg/kg |  |  | 3 mg/kg | 6 mg/kg
Response | Placebo + MTX | q8 wks | q4 wks | q8 wks | q4 wks | Placebo + MTX | q8 wks | q8 wks
 | (n = 88) | (n = 86) | (n = 86) | (n = 87) | (n = 81) | (n = 274) | (n = 351) | (n = 355)
ACR 20
Week 30 | 20% | 50% [P≤0.001] | 50% | 52% | 58% | N/A | N/A | N/A
Week 54 | 17% | 42% | 48% | 59% | 59% | 54% | 62% [P<0.05] | 66%
ACR 50
Week 30 | 5% | 27% | 29% | 31% | 26% | N/A | N/A | N/A
Week 54 | 9% | 21% | 34% | 40% | 38% | 32% | 46% | 50%
ACR 70
Week 30 | 0% | 8% [P<0.01] | 11% | 18% | 11% | N/A | N/A | N/A
Week 54 | 2% | 11% | 18% | 26% | 19% | 21% | 33% | 37%
Major clinical response [A major clinical response was defined as a 70% ACR response for 6 consecutive months (consecutive visits spanning at least 26 weeks) through Week 102 for Study RA I and Week 54 for Study RA II.] | 0% | 7% | 8% | 15% | 6% | 8% | 12% | 17%

Table 8: Components of ACR 20 at baseline and 54 weeks (Study RA I)
 | Placebo + MTX |  | Infliximab + MTX [All doses/schedules of infliximab + MTX]
Parameter (medians) | (n = 88) |  | (n = 340)
 | Baseline | Week 54 | Baseline | Week 54
No. of Tender Joints | 24 | 16 | 32 | 8
No. of Swollen Joints | 19 | 13 | 20 | 7
Pain [Visual Analog Scale (0=best, 10=worst)] | 6.7 | 6.1 | 6.8 | 3.3
Physician's Global Assessment | 6.5 | 5.2 | 6.2 | 2.1
Patient's Global Assessment | 6.2 | 6.2 | 6.3 | 3.2
Disability Index (HAQ-DI) [Health Assessment Questionnaire, measurement of 8 categories: dressing and grooming, arising, eating, walking, hygiene, reach, grip, and activities (0=best, 3=worst)] | 1.8 | 1.5 | 1.8 | 1.3
CRP (mg/dL) | 3.0 | 2.3 | 2.4 | 0.6

Radiographic Response

Structural damage in both hands and feet was assessed radiographically at Week 54 by the change from baseline in the van der Heijde-modified Sharp (vdH-S) score, a composite score of structural damage that measures the number and size of joint erosions and the degree of joint space narrowing in hands/wrists and feet.

In Study RA I, approximately 80% of patients had paired X-ray data at 54 weeks and approximately 70% at 102 weeks. The inhibition of progression of structural damage was observed at 54 weeks (Table 9) and maintained through 102 weeks.

In Study RA II, >90% of patients had at least 2 evaluable X-rays. Inhibition of progression of structural damage was observed at Weeks 30 and 54 (Table 9) in the infliximab + MTX groups compared to MTX alone. Patients treated with infliximab + MTX demonstrated less progression of structural damage compared to MTX alone, whether baseline acute phase reactants (ESR and CRP) were normal or elevated: patients with elevated baseline acute phase reactants treated with MTX alone demonstrated a mean progression in vdH-S score of 4.2 units compared to patients treated with infliximab + MTX who demonstrated 0.5 units of progression; patients with normal baseline acute phase reactants treated with MTX alone demonstrated a mean progression in vdH-S score of 1.8 units compared to infliximab + MTX who demonstrated 0.2 units of progression. Of patients receiving infliximab + MTX, 59% had no progression (vdH-S score ≤0 unit) of structural damage compared to 45% of patients receiving MTX alone. In a subset of patients who began the study without erosions, infliximab + MTX maintained an erosion-free state at 1-year in a greater proportion of patients than MTX alone, 79% (77/98) vs. 58% (23/40), respectively (P < 0.01). Fewer patients in the infliximab + MTX groups (47%) developed erosions in uninvolved joints compared to MTX alone (59%).

Table 9: Radiographic Change from Baseline to Week 54 in Adult RA Patients (Studies RA I and RA II)
 | Study RA I |  |  | Study RA II
 |  | Infliximab + MTX |  |  | Infliximab + MTX
 |  | 3 mg/kg | 10 mg/kg |  | 3 mg/kg | 6 mg/kg
 | Placebo + MTX | q8 wks | q8 wks | Placebo + MTX | q8 wks | q8 wks
 | (n = 64) | (n = 71) | (n = 77) | (n = 282) | (n = 359) | (n = 363)
Total Score
Baseline
Mean | 79 | 78 | 65 | 11.3 | 11.6 | 11.2
Median | 55 | 57 | 56 | 5.1 | 5.2 | 5.3
Change from baseline
Mean | 6.9 | 1.3 [P<0.001 for each outcome against placebo.] | 0.2 | 3.7 | 0.4 | 0.5
Median | 4.0 | 0.5 | 0.5 | 0.4 | 0.0 | 0.0
Erosion Score
Baseline
Mean | 44 | 44 | 33 | 8.3 | 8.8 | 8.3
Median | 25 | 29 | 22 | 3.0 | 3.8 | 3.8
Change from baseline
Mean | 4.1 | 0.2 | 0.2 | 3.0 | 0.3 | 0.1
Median | 2.0 | 0.0 | 0.5 | 0.3 | 0.0 | 0.0
JSN Score
Baseline
Mean | 36 | 34 | 31 | 3.0 | 2.9 | 2.9
Median | 26 | 29 | 24 | 1.0 | 1.0 | 1.0
Change from baseline
Mean | 2.9 | 1.1 | 0.0 | 0.6 | 0.1 | 0.2
Median | 1.5 | 0.0 | 0.0 | 0.0 | 0.0 | 0.0

Physical Function Response

Physical function and disability were assessed using the Health Assessment Questionnaire (HAQ-DI) and the general health-related quality of life questionnaire SF-36.

In Study RA I, all doses/schedules of infliximab + MTX showed significantly greater improvement from baseline in HAQ-DI and SF-36 physical component summary score averaged over time through Week 54 compared to placebo + MTX, and no worsening in the SF-36 mental component summary score. The median (interquartile range) improvement from baseline to Week 54 in HAQ-DI was 0.1 (-0.1, 0.5) for the placebo + MTX group and 0.4 (0.1, 0.9) for infliximab + MTX (p < 0.001). Both HAQ-DI and SF-36 effects were maintained through Week 102. Approximately 80% of patients in all doses/schedules of infliximab + MTX remained in the trial through 102 weeks.

In Study RA II, both infliximab treatment groups showed greater improvement in HAQ-DI from baseline averaged over time through Week 54 compared to MTX alone; 0.7 for infliximab + MTX vs. 0.6 for MTX alone (P ≤ 0.001). No worsening in the SF-36 mental component summary score was observed.

14.6 Ankylosing Spondylitis

The safety and efficacy of infliximab were assessed in a randomized, multicenter, double-blind, placebo-controlled study in 279 adult patients with active AS. Patients were between 18 and 74 years of age, and had AS as defined by the modified New York criteria for Ankylosing Spondylitis. Patients were to have had active disease as evidenced by both a Bath Ankylosing Spondylitis Disease Activity Index (BASDAI) score >4 (possible range 0-10) and spinal pain >4 (on a Visual Analog Scale [VAS] of 0-10). Patients with complete ankylosis of the spine were excluded from study participation, and the use of Disease-Modifying Anti-Rheumatic Drugs (DMARDs) and systemic corticosteroids were prohibited. Doses of 5 mg/kg of infliximab or placebo were administered intravenously at Weeks 0, 2, 6, 12 and 18.

At 24 weeks, improvement in the signs and symptoms of AS, as measured by the proportion of patients achieving a 20% improvement in ASAS response criteria (ASAS 20), was seen in 60% of patients in the infliximab-treated group vs. 18% of patients in the placebo group (p < 0.001). Improvement was observed at Week 2 and maintained through Week 24 (Figure 3 and Table 10).

Figure 3: Proportion of Adult AS Patients Who Achieved a ASAS 20 Response

At 24 weeks, the proportions of patients achieving a 50% and a 70% improvement in the signs and symptoms of AS, as measured by ASAS response criteria (ASAS 50 and ASAS 70, respectively), were 44% and 28%, respectively, for patients receiving infliximab, compared to 9% and 4%, respectively, for patients receiving placebo (P < 0.001, infliximab vs. placebo). A low level of disease activity (defined as a value <20 [on a scale of 0-100 mm] in each of the 4 ASAS response parameters) was achieved in 22% of infliximab-treated patients vs. 1% in placebo-treated patients (P < 0.001).

Table 10: Components of AS Disease Activity
 | Placebo (n = 78) |  | Infliximab 5 mg/kg (n = 201)
 | Baseline | 24 Weeks | Baseline | 24 Weeks | P-value
ASAS 20 response
Criteria (Mean)
Patient Global Assessment [Measured on a VAS with 0= "none" and 10= "severe"] | 6.6 | 6.0 | 6.8 | 3.8 | <0.001
Spinal pain | 7.3 | 6.5 | 7.6 | 4.0 | <0.001
BASFI [Bath Ankylosing Spondylitis Functional Index (BASFI), average of 10 questions] | 5.8 | 5.6 | 5.7 | 3.6 | <0.001
Inflammation [Inflammation, average of last 2 questions on the 6-question BASDAI] | 6.9 | 5.8 | 6.9 | 3.4 | <0.001
Acute Phase Reactants
Median CRP [CRP normal range 0-1.0 mg/dL] (mg/dL) | 1.7 | 1.5 | 1.5 | 0.4 | <0.001
Spinal Mobility (cm, Mean)
Modified Schober's test [Spinal mobility normal values: modified Schober's test: >4 cm; chest expansion: >6 cm; tragus to wall: <15 cm; lateral spinal flexion: >10 cm] | 4.0 | 5.0 | 4.3 | 4.4 | 0.75
Chest expansion | 3.6 | 3.7 | 3.3 | 3.9 | 0.04
Tragus to wall | 17.3 | 17.4 | 16.9 | 15.7 | 0.02
Lateral spinal flexion | 10.6 | 11.0 | 11.4 | 12.9 | 0.03

The median improvement from baseline in the general health-related quality-of-life questionnaire SF-36 physical component summary score at Week 24 was 10.2 for the infliximab group vs. 0.8 for the placebo group (P < 0.001). There was no change in the SF-36 mental component summary score in either the infliximab group or the placebo group.

Results of this study were similar to those seen in a multicenter double-blind, placebo-controlled study of 70 patients with AS.

14.7 Psoriatic Arthritis

Safety and efficacy of infliximab were assessed in a multicenter, double-blind, placebo-controlled study in 200 adult patients with active PsA despite DMARD or NSAID therapy (≥5 swollen joints and ≥5 tender joints) with 1 or more of the following subtypes: arthritis involving DIP joints (n = 49), arthritis mutilans (n = 3), asymmetric peripheral arthritis (n = 40), polyarticular arthritis (n = 100), and spondylitis with peripheral arthritis (n = 8). Patients also had Ps with a qualifying target lesion ≥2 cm in diameter. Forty-six percent of patients continued on stable doses of methotrexate (≤25 mg/week). During the 24-week double-blind phase, patients received either 5 mg/kg infliximab or placebo at Weeks 0, 2, 6, 14, and 22 (100 patients in each group). At Week 16, placebo patients with <10% improvement from baseline in both swollen and tender joint counts were switched to infliximab induction (early escape). At Week 24, all placebo-treated patients crossed over to infliximab induction. Dosing continued for all patients through Week 46.

Clinical Response

Treatment with infliximab resulted in improvement in signs and symptoms, as assessed by the ACR criteria, with 58% of infliximab-treated patients achieving ACR 20 at Week 14, compared with 11% of placebo-treated patients (P < 0.001). The response was similar regardless of concomitant use of methotrexate. Improvement was observed as early as Week 2. At 6 months, the ACR 20/50/70 responses were achieved by 54%, 41%, and 27%, respectively, of patients receiving infliximab compared to 16%, 4%, and 2%, respectively, of patients receiving placebo. Similar responses were seen in patients with each of the subtypes of PsA, although few patients were enrolled with the arthritis mutilans and spondylitis with peripheral arthritis subtypes.

Compared to placebo, treatment with infliximab resulted in improvements in the components of the ACR response criteria, as well as in dactylitis and enthesopathy (Table 11). The clinical response was maintained through Week 54. Similar ACR responses were observed in an earlier randomized, placebo-controlled study of 104 PsA patients, and the responses were maintained through 98 weeks in an open-label extension phase.

Table 11: Components of ACR 20 and Percentage of Adult PsA Patients with 1 or More Joints with Dactylitis and Percentage of Adult PsA Patients with Enthesopathy at Baseline and Week 24
 | Placebo |  | Infliximab 5 mg/kg [P<0.001 for percent change from baseline in all components of ACR 20 at Week 24, P<0.05 for % of patients with dactylitis, and P=0.004 for % of patients with enthesopathy at Week 24]
Patients Randomized | (n = 100) |  | (n = 100)
 | Baseline | Week 24 | Baseline | Week 24
Parameter (medians)
No. of Tender Joints [Scale 0-68] | 24 | 20 | 20 | 6
No. of Swollen Joints [Scale 0-66] | 12 | 9 | 12 | 3
Pain [Visual Analog Scale (0=best, 10=worst)] | 6.4 | 5.6 | 5.9 | 2.6
Physician's Global Assessment | 6.0 | 4.5 | 5.6 | 1.5
Patient's Global Assessment | 6.1 | 5.0 | 5.9 | 2.5
Disability Index (HAQ-DI) [Health Assessment Questionnaire, measurement of 8 categories: dressing and grooming, arising, eating, walking, hygiene, reach, grip, and activities (0=best, 3=worst)] | 1.1 | 1.1 | 1.1 | 0.5
CRP (mg/dL) [Normal range 0-0.6 mg/dL] | 1.2 | 0.9 | 1.0 | 0.4
% Patients with 1 or more digits with dactylitis | 41 | 33 | 40 | 15
% Patients with enthesopathy | 35 | 36 | 42 | 22

Improvement in Psoriasis Area and Severity Index (PASI) in PsA patients with baseline body surface area (BSA) ≥3% (n = 87 placebo, n = 83 infliximab) was achieved at Week 14, regardless of concomitant methotrexate use, with 64% of infliximab-treated patients achieving at least 75% improvement from baseline vs. 2% of placebo-treated patients; improvement was observed in some patients as early as Week 2. At 6 months, the PASI 75 and PASI 90 responses were achieved by 60% and 39%, respectively, of patients receiving infliximab compared to 1% and 0%, respectively, of patients receiving placebo. The PASI response was generally maintained through Week 54. [see Clinical Studies (14.8)].

Radiographic Response

Structural damage in both hands and feet was assessed radiographically by the change from baseline in the van der Heijde-Sharp (vdH-S) score, modified by the addition of hand DIP joints. The total modified vdH-S score is a composite score of structural damage that measures the number and size of joint erosions and the degree of joint space narrowing (JSN) in the hands and feet. At Week 24, infliximab-treated patients had less radiographic progression than placebo-treated patients (mean change of −0.70 vs. 0.82, P < 0.001). Infliximab-treated patients also had less progression in their erosion scores (−0.56 vs 0.51) and JSN scores (−0.14 vs 0.31). The patients in the infliximab group demonstrated continued inhibition of structural damage at Week 54. Most patients showed little or no change in the vdH-S score during this 12-month study (median change of 0 in both patients who initially received infliximab or placebo). More patients in the placebo group (12%) had readily apparent radiographic progression compared with the infliximab group (3%).

Physical Function

Physical function status was assessed using the HAQ Disability Index (HAQ-DI) and the SF-36 Health Survey. Infliximab-treated patients demonstrated significant improvement in physical function as assessed by HAQ-DI (median percent improvement in HAQ-DI score from baseline to Week 14 and 24 of 43% for infliximab-treated patients vs 0% for placebo-treated patients).

During the placebo-controlled portion of the trial (24 weeks), 54% of infliximab-treated patients achieved a clinically meaningful improvement in HAQ-DI (≥0.3 unit decrease) compared to 22% of placebo-treated patients. Infliximab-treated patients also demonstrated greater improvement in the SF-36 physical and mental component summary scores than placebo-treated patients. The responses were maintained for up to 2 years in an open-label extension study.

14.8 Plaque Psoriasis

The safety and efficacy of infliximab were assessed in 3 randomized, double-blind, placebo-controlled studies in patients 18 years of age and older with chronic, stable Ps involving ≥10% BSA, a minimum PASI score of 12, and who were candidates for systemic therapy or phototherapy. Patients with guttate, pustular, or erythrodermic psoriasis were excluded from these studies. No concomitant anti-psoriatic therapies were allowed during the study, with the exception of low-potency topical corticosteroids on the face and groin after Week 10 of study initiation.

Study I (EXPRESS) evaluated 378 patients who received placebo or infliximab at a dose of 5 mg/kg at Weeks 0, 2, and 6 (induction therapy), followed by maintenance therapy every 8 weeks. At Week 24, the placebo group crossed over to infliximab induction therapy (5 mg/kg), followed by maintenance therapy every 8 weeks. Patients originally randomized to infliximab continued to receive infliximab 5 mg/kg every 8 weeks through Week 46. Across all treatment groups, the median baseline PASI score was 21 and the baseline Static Physician Global Assessment (sPGA) score ranged from moderate (52% of patients) to marked (36%) to severe (2%). In addition, 75% of patients had a BSA >20%. Seventy-one percent of patients previously received systemic therapy, and 82% received phototherapy.

Study II (EXPRESS II) evaluated 835 patients who received placebo or infliximab at doses of 3 mg/kg or 5 mg/kg at Weeks 0, 2, and 6 (induction therapy). At Week 14, within each infliximab dose group, patients were randomized to either scheduled (every 8 weeks) or as needed (PRN) maintenance treatment through Week 46. At Week 16, the placebo group crossed over to infliximab induction therapy (5 mg/kg), followed by maintenance therapy every 8 weeks. Across all treatment groups, the median baseline PASI score was 18, and 63% of patients had a BSA >20%. Fifty-five percent of patients previously received systemic therapy, and 64% received a phototherapy.

Study III (SPIRIT) evaluated 249 patients who had previously received either psoralen plus ultraviolet A treatment (PUVA) or other systemic therapy for their psoriasis. These patients were randomized to receive either placebo or infliximab at doses of 3 mg/kg or 5 mg/kg at Weeks 0, 2, and 6. At Week 26, patients with a sPGA score of moderate or worse (greater than or equal to 3 on a scale of 0 to 5) received an additional dose of the randomized treatment. Across all treatment groups, the median baseline PASI score was 19, and the baseline sPGA score ranged from moderate (62% of patients) to marked (22%) to severe (3%). In addition, 75% of patients had a BSA >20%. Of the enrolled patients, 114 (46%) received the Week 26 additional dose.

In Studies I, II and III, the primary endpoint was the proportion of patients who achieved a reduction in score of at least 75% from baseline at Week 10 by the PASI (PASI 75). In Study I and Study III, another evaluated outcome included the proportion of patients who achieved a score of "cleared" or "minimal" by the sPGA. The sPGA is a 6-category scale ranging from "5 = severe" to "0 = cleared" indicating the physician's overall assessment of the psoriasis severity focusing on induration, erythema, and scaling. Treatment success, defined as "cleared" or "minimal," consisted of none or minimal elevation in plaque, up to faint red coloration in erythema, and none or minimal fine scale over <5% of the plaque.

Study II also evaluated the proportion of patients who achieved a score of "clear" or "excellent" by the relative Physician's Global Assessment (rPGA). The rPGA is a 6-category scale ranging from "6 = worse" to "1 = clear" that was assessed relative to baseline. Overall lesions were graded with consideration to the percent of body involvement as well as overall induration, scaling, and erythema. Treatment success, defined as "clear" or "excellent," consisted of some residual pinkness or pigmentation to marked improvement (nearly normal skin texture; some erythema may be present). The results of these studies are presented in Table 12.

Table 12: Adult Psoriasis Studies I, II, and III, Percentage of Patients Who Achieved PASI 75 and Percentage Who Achieved Treatment "Success" with Physician's Global Assessment at Week 10
 | Placebo | Infliximab
 |  | 3 mg/kg | 5 mg/kg
Psoriasis Study I - patients randomized [Patients with missing data at Week 10 were considered as nonresponders.] | 77 | — | 301
PASI 75 | 2 (3%) | — | 242 (80%) [P<0.001 compared with placebo.]
sPGA | 3 (4%) | — | 242 (80%)
Psoriasis Study II - patients randomized | 208 | 313 | 314
PASI 75 | 4 (2%) | 220 (70%) | 237 (75%)
rPGA | 2 (1%) | 217 (69%) | 234 (75%)
Psoriasis Study III - patients randomized [Patients with missing data at Week 10 were imputed by last observation.] | 51 | 99 | 99
PASI 75 | 3 (6%) | 71 (72%) | 87 (88%)
sPGA | 5 (10%) | 71 (72%) | 89 (90%)

In Study I, in the subgroup of patients with more extensive Ps who had previously received phototherapy, 85% of patients on 5 mg/kg infliximab achieved a PASI 75 at Week 10 compared with 4% of patients on placebo.

In Study II, in the subgroup of patients with more extensive Ps who had previously received phototherapy, 72% and 77% of patients on 3 mg/kg and 5 mg/kg infliximab achieved a PASI 75 at Week 10 respectively compared with 1% on placebo. In Study II, among patients with more extensive Ps who had failed or were intolerant to phototherapy, 70% and 78% of patients on 3 mg/kg and 5 mg/kg infliximab achieved a PASI 75 at Week 10 respectively, compared with 2% on placebo.

Maintenance of response was studied in a subset of 292 and 297 infliximab-treated patients in the 3 mg/kg and 5 mg/kg groups; respectively, in Study II. Stratified by PASI response at Week 10 and investigational site, patients in the active treatment groups were re-randomized to either a scheduled or as needed maintenance (PRN) therapy, beginning on Week 14.

The groups that received a maintenance dose every 8 weeks appear to have a greater percentage of patients maintaining a PASI 75 through Week 50 as compared to patients who received the as needed or PRN doses, and the best response was maintained with the 5 mg/kg every 8-week dose. These results are shown in Figure 4. At Week 46, when infliximab serum concentrations were at trough level, in the every 8-week dose group, 54% of patients in the 5 mg/kg group compared to 36% in the 3 mg/kg group achieved PASI 75. The lower percentage of PASI 75 responders in the 3 mg/kg every 8-week dose group compared to the 5 mg/kg group was associated with a lower percentage of patients with detectable trough serum infliximab levels. This may be related in part to higher antibody rates [see Adverse Reactions (6.1)]. In addition, in a subset of patients who had achieved a response at Week 10, maintenance of response appears to be greater in patients who received infliximab every 8 weeks at the 5 mg/kg dose. Regardless of whether the maintenance doses are PRN or every 8 weeks, there is a decline in response in a subpopulation of patients in each group over time. The results of Study I through Week 50 in the 5 mg/kg every 8 weeks maintenance dose group were similar to the results from Study II.

Figure 4: Proportion of Adult Ps Patients Who Achieved ≥75% Improvement in PASI from Baseline through Week 50 (patients randomized at Week 14)

Efficacy and safety of infliximab treatment beyond 50 weeks have not been evaluated in patients with Ps.

15 REFERENCES

1. Turner D, Otley AR, Mack D, et al. Development, validation, and evaluation of a pediatric ulcerative colitis activity index: A prospective multicenter study. Gastroenterology. 2007;133:423–432.

16 HOW SUPPLIED/STORAGE AND HANDLING

How Supplied

AVSOLA (infliximab-axxq) for injection is supplied as one single-dose vial individually packaged in a carton (NDC 55513-670-01, 55513-670-21). Each single-dose vial contains 100 mg of infliximab-axxq as a sterile, preservative-free, white to slightly yellow lyophilized powder for reconstitution and dilution (more than one vial may be needed for a full dose) [see Dosage and Administration (2.11)].

Storage and Handling

Store unopened AVSOLA vials in a refrigerator at 2°C to 8°C (36°F to 46°F). Protect from light.

If needed, unopened AVSOLA vials may be stored at room temperatures up to a maximum of 30°C (86°F) for a single period of up to 6 months but not exceeding the original expiration date. The new expiration date must be written in the space provided on the carton. Once removed from the refrigerator AVSOLA cannot be returned to the refrigerator.

For storage conditions of the reconstituted and diluted product, see Dosage and Administration (2.11).

17 PATIENT COUNSELING INFORMATION

Advise the patient or their caregiver to read the FDA-approved patient labeling (Medication Guide).

Patients or their caregivers should be advised of the potential benefits and risks of AVSOLA. Healthcare providers should instruct their patients or their caregivers to read the Medication Guide before starting AVSOLA therapy and to reread it each time they receive an infusion.

Infections

Inform patients that AVSOLA increases the risk for developing serious infections. Instruct patients of the importance of contacting their healthcare provider if they develop any symptoms of an infection, including tuberculosis, invasive fungal infections, and reactivation of hepatitis B virus infections [see Warnings and Precautions (5.1, 5.3)].

Malignancies

Malignancies have been reported among children, adolescents and young adults who received treatment with TNF blockers. Patients should be counseled about the risk of lymphoma and other malignancies while receiving AVSOLA [see Warnings and Precautions (5.2)].

Hepatotoxicity

Instruct patients to seek medical attention if they develop signs or symptoms of hepatotoxicity (e.g., jaundice) [see Warnings and Precautions (5.4)].

Heart Failure

Instruct patients to seek medical attention and consult their prescriber if they develop signs or symptoms of heart failure [see Contraindications (4) and Warnings and Precautions (5.5)].

Hematologic Reactions

Instruct patients to seek immediate medical attention if they develop signs and symptoms suggestive of blood dyscrasias or infection (e.g., persistent fever) while on AVSOLA [see Warnings and Precautions (5.6)].

Hypersensitivity

Advise patients to seek immediate medical attention if they experience any symptoms of serious hypersensitivity reactions [see Warnings and Precautions (5.7)].

Cardiovascular and Cerebrovascular Reactions During and After Infusion

Advise patients to seek immediate medical attention if they develop any new or worsening symptoms of cardiovascular and cerebrovascular reactions which have been reported during and within 24 hours of initiation of AVSOLA infusion [see Warnings and Precautions (5.8)].

Neurologic Reactions

Advise patients to seek medical attention if they develop signs or symptoms of neurologic reactions [see Warnings and Precautions (5.9)].

Live Vaccines/Therapeutic Infectious Agents

Instruct patients treated with AVSOLA to avoid receiving live vaccines or therapeutic infectious agents [see Warnings and Precautions (5.13)].

AVSOLA® (infliximab-axxq)

Manufactured by:
Amgen, Inc.
One Amgen Center Drive
Thousand Oaks, CA 91320-1799
U.S. License No. 1080

AMGEN and AVSOLA (infliximab-axxq) are trademarks owned or licensed by Amgen, Inc. its subsidiaries, or affiliates.

© 2019, 2021, 2025 Amgen, Inc. All rights reserved
[part number] v4

MEDICATION GUIDE
AVSOLA® (av-SOH-luh)
(infliximab-axxq)
for injection, for intravenous use

Read the Medication Guide that comes with AVSOLA before you receive the first treatment, and before each time you get a treatment of AVSOLA. This Medication Guide does not take the place of talking with your doctor about your medical condition or treatment.
What is the most important information I should know about AVSOLA?
AVSOLA may cause serious side effects, including:
1. Risk of infection
AVSOLA is a medicine that affects your immune system. AVSOLA can lower the ability of your immune system to fight infections. Serious infections have happened in patients receiving AVSOLA. These infections include tuberculosis (TB) and infections caused by viruses, fungi or bacteria that have spread throughout the body. Some patients have died from these infections.

- Your doctor should test you for TB before starting AVSOLA.
- Your doctor should monitor you closely for signs and symptoms of TB during treatment with AVSOLA.

Before starting AVSOLA, tell your doctor if you:

- think you have an infection. You should not start receiving AVSOLA if you have any kind of infection.
- are being treated for an infection.
- have signs of an infection, such as a fever, cough, flu-like symptoms.
- have any open cuts or sores on your body.
- get a lot of infections or have infections that keep coming back.
- have diabetes or an immune system problem. People with these conditions have a higher chance for infections.
- have TB, or have been in close contact with someone with TB.
- live or have lived in certain parts of the country (such as the Ohio and Mississippi River valleys) where there is an increased risk for getting certain kinds of fungal infections (histoplasmosis, coccidioidomycosis, or blastomycosis). These infections may develop or become more severe if you receive AVSOLA. If you do not know if you have lived in an area where histoplasmosis, coccidioidomycosis, or blastomycosis is common, ask your doctor.
- have or have had hepatitis B.
- use the medicines KINERET (anakinra), ORENCIA (abatacept), ACTEMRA (tocilizumab), or other medicines called biologics used to treat the same conditions as AVSOLA.

After starting AVSOLA, if you have an infection, any sign of an infection including a fever, cough, flu-like symptoms, or have open cuts or sores on your body, call your doctor right away. AVSOLA can make you more likely to get infections or make any infection that you have worse.
2. Risk of Cancer

- There have been cases of unusual cancers in children and teenage patients using tumor necrosis factor (TNF) blocker medicines, such as AVSOLA.
- For children and adults receiving TNF blocker medicines, including AVSOLA, the chances of getting lymphoma or other cancers may increase.
- Some people receiving TNF blockers, including AVSOLA, developed a rare type of cancer called hepatosplenic T-cell lymphoma. This type of cancer often results in death. Most of these people were male teenagers or young men. Also, most people were being treated for Crohn's disease or ulcerative colitis with a TNF blocker and another medicine called azathioprine or 6-mercaptopurine.
- People who have been treated for rheumatoid arthritis, Crohn's disease, ulcerative colitis, ankylosing spondylitis, psoriatic arthritis and plaque psoriasis for a long time may be more likely to develop lymphoma. This is especially true for people with very active disease.
- Some people treated with infliximab products, such as AVSOLA, have developed certain kinds of skin cancer. If any changes in the appearance of your skin or growths on your skin occur during or after your treatment with AVSOLA, tell your doctor.
- Patients with Chronic Obstructive Pulmonary Disease (COPD), a specific type of lung disease, may have an increased risk for getting cancer while being treated with AVSOLA.
- Some women being treated for rheumatoid arthritis with infliximab products have developed cervical cancer. For women receiving AVSOLA, including those over 60 years of age, your doctor may recommend that you continue to be regularly screened for cervical cancer.
- Tell your doctor if you have ever had any type of cancer. Discuss with your doctor any need to adjust medicines you may be taking.

See the section "What are the possible side effects of AVSOLA?" below for more information.

What is AVSOLA?
AVSOLA is a prescription medicine that is approved for patients with:

- Rheumatoid Arthritis - adults with moderately to severely active rheumatoid arthritis, along with the medicine methotrexate.
- Crohn's Disease - children 6 years and older and adults with Crohn's disease who have not responded well to other medicines.
- Ankylosing Spondylitis in adults.
- Psoriatic Arthritis in adults.
- Plaque Psoriasis - adult patients with plaque psoriasis that is chronic (does not go away), severe, extensive, and/or disabling.
- Ulcerative Colitis - children 6 years and older and adults with moderately to severely active ulcerative colitis who have not responded well to other medicines.

AVSOLA blocks the action of a protein in your body called tumor necrosis factor-alpha (TNF-alpha). TNF-alpha is made by your body's immune system. People with certain diseases have too much TNF-alpha that can cause the immune system to attack normal healthy parts of the body. AVSOLA can block the damage caused by too much TNF-alpha.
It is not known if AVSOLA is safe and effective in children under 6 years of age.

Who should not receive AVSOLA?
You should not receive AVSOLA if you have:

- heart failure, unless your doctor has examined you and decided that you are able to receive AVSOLA. Talk to your doctor about your heart failure.
- had an allergic reaction to infliximab products, or any of the ingredients in AVSOLA. See the end of this Medication Guide for a complete list of ingredients in AVSOLA.

What should I tell my doctor before starting treatment with AVSOLA?
Your doctor will assess your health before each treatment.
Tell your doctor about all of your medical conditions, including if you:

- have an infection (see "What is the most important information I should know about AVSOLA?").
- have other liver problems including liver failure.
- have heart failure or other heart conditions. If you have heart failure, it may get worse while you receive AVSOLA.
- have or have had any type of cancer.
- have had phototherapy (treatment with ultraviolet light or sunlight along with a medicine to make your skin sensitive to light) for psoriasis. You may have a higher chance of getting skin cancer while receiving AVSOLA.
- have COPD, a specific type of lung disease. Patients with COPD may have an increased risk of getting cancer while receiving AVSOLA.
- have or have had a condition that affects your nervous system such as:
  - multiple sclerosis, or Guillain-Barré syndrome, or
  - if you experience any numbness or tingling, or
  - if you have had a seizure.
- have recently received or are scheduled to receive a vaccine. Adults and children receiving AVSOLA should not receive live vaccines (for example, the Bacille Calmette-Guérin [BCG] vaccine) or treatment with a weakened bacteria (such as BCG for bladder cancer). Adults and children should have all of their vaccines brought up to date before starting treatment with AVSOLA.
- are pregnant or plan to become pregnant, are breastfeeding or plan to breastfeed. You and your doctor should decide if you should receive AVSOLA while you are pregnant or breastfeeding.

If you have a baby and you were receiving AVSOLA during your pregnancy, it is important to tell your baby's doctor and other health care professionals about your AVSOLA use so they can decide when your baby should receive any vaccine. Certain vaccinations can cause infections.
If you received AVSOLA while you were pregnant, your baby may be at higher risk for getting an infection. If your baby receives a live vaccine within 6 months after birth, your baby may develop infections with serious complications that can lead to death. This includes live vaccines such as the BCG, rotavirus, or any other live vaccines. For other types of vaccines, talk with your doctor.

How should I receive AVSOLA?

- You will be given AVSOLA through a needle placed in a vein (IV or intravenous infusion) in your arm.
- Your doctor may decide to give you medicine before starting the AVSOLA infusion to prevent or lessen side effects.
- Only a healthcare professional should prepare the medicine and administer it to you.
- AVSOLA will be given to you over a period of about 2 hours.
- If you have side effects from AVSOLA, the infusion may need to be adjusted or stopped. In addition, your healthcare professional may decide to treat your symptoms.
- A healthcare professional will monitor you during the AVSOLA infusion and for a period of time afterward for side effects. Your doctor may do certain tests while you are receiving AVSOLA to monitor you for side effects and to see how well you respond to the treatment.
- Your doctor will determine the right dose of AVSOLA for you and how often you should receive it. Make sure to discuss with your doctor when you will receive infusions and to come in for all your infusions and follow-up appointments.

What should I avoid while receiving AVSOLA?
Do not take AVSOLA together with medicines such as KINERET (anakinra), ORENCIA (abatacept), ACTEMRA (tocilizumab), or other medicines called biologics that are used to treat the same conditions as AVSOLA.
Tell your doctor about all the medicines you take, including prescription and over-the-counter medicines, vitamins, and herbal supplements. These include any other medicines to treat Crohn's disease, ulcerative colitis, rheumatoid arthritis, ankylosing spondylitis, psoriatic arthritis or psoriasis.
Know the medicines you take. Keep a list of your medicines and show them to your doctor and pharmacist when you get a new medicine.

What are the possible side effects of AVSOLA?
AVSOLA can cause serious side effects, including:
See "What is the most important information I should know about AVSOLA?"
Serious Infections

- Some patients, especially those 65 years and older have had serious infections while receiving infliximab products, such as AVSOLA. These serious infections include TB and infections caused by viruses, fungi, or bacteria that have spread throughout the body or cause infections in certain areas (such as skin). Some patients die from these infections. If you get an infection while receiving treatment with AVSOLA your doctor will treat your infection and may need to stop your AVSOLA treatment.
- Tell your doctor right away if you have any of the following signs of an infection while receiving or after receiving AVSOLA:

- a fever
- feel very tired
- have a cough

- have flu-like symptoms
- warm, red, or painful skin

- Your doctor will examine you for TB and perform a test to see if you have TB. If your doctor feels that you are at risk for TB, you may be treated with medicine for TB before you begin treatment with AVSOLA and during treatment with AVSOLA.
- Even if your TB test is negative, your doctor should carefully monitor you for TB infections while you are receiving AVSOLA. Patients who had a negative TB skin test before receiving infliximab products have developed active TB.
- If you are a chronic carrier of the hepatitis B virus, the virus can become active while you are being treated with AVSOLA. In some cases, patients have died as a result of hepatitis B virus being reactivated. Your doctor should do a blood test for hepatitis B virus before you start treatment with AVSOLA and occasionally while you are being treated. Tell your doctor if you have any of the following symptoms:

- feel unwell
- poor appetite

- tiredness (fatigue)
- fever, skin rash, or joint pain

Heart Failure
If you have a heart problem called congestive heart failure, your doctor should check you closely while you are receiving AVSOLA. Your congestive heart failure may get worse while you are receiving AVSOLA. Be sure to tell your doctor of any new or worse symptoms including:

- shortness of breath
- swelling of ankles or feet

- sudden weight gain

Treatment with AVSOLA may need to be stopped if you get new or worse congestive heart failure.
Other Heart Problems
Some patients have experienced a heart attack (some of which led to death), low blood flow to the heart, or abnormal heart rhythm within 24 hours of beginning their infusion of infliximab products. Symptoms may include chest discomfort or pain, arm pain, stomach pain, shortness of breath, anxiety, lightheadedness, dizziness, fainting, sweating, nausea, vomiting, fluttering or pounding in your chest, and/or a fast or a slow heartbeat. Tell your doctor right away if you have any of these symptoms.
Liver Injury
Some patients receiving infliximab products have developed serious liver problems. Tell your doctor if you have:

- jaundice (skin and eyes turning yellow)
- dark brown-colored urine
- pain on the right side of your stomach area (right-sided abdominal pain)

- fever
- extreme tiredness (severe fatigue)

Blood Problems
In some patients receiving infliximab products, the body may not make enough of the blood cells that help fight infections or help stop bleeding. Tell your doctor if you:

- have a fever that does not go away
- bruise or bleed very easily

- look very pale

Nervous System Disorders
Some patients receiving infliximab products have developed problems with their nervous system. Tell your doctor if you have:

- changes in your vision
- numbness or tingling in any part of your body

- seizures
- weakness in your arms or legs

Some patients have experienced a stroke within approximately 24 hours of their infusion with infliximab products. Tell your doctor right away if you have symptoms of a stroke which may include: numbness or weakness of the face, arm or leg, especially on one side of the body; sudden confusion, trouble speaking or understanding; sudden trouble seeing in one or both eyes, sudden trouble walking, dizziness, loss of balance or coordination or a sudden, severe headache.

Allergic Reactions
Some patients have had allergic reactions to infliximab products. Some of these reactions were severe. These reactions can happen while you are getting your AVSOLA treatment or shortly afterward. Your doctor may need to stop or pause your treatment with AVSOLA and may give you medicines to treat the allergic reaction. Signs of an allergic reaction can include:

- hives (red, raised, itchy patches of skin)
- difficulty breathing
- chest pain

- high or low blood pressure
- fever
- chills

Some patients treated with infliximab products have had delayed allergic reactions. The delayed reactions occurred 3 to 12 days after receiving treatment with infliximab products. Tell your doctor right away if you have any of these signs of delayed allergic reaction to AVSOLA:

- fever
- rash
- headache
- sore throat

- muscle or joint pain
- swelling of the face and hands
- difficulty swallowing

Lupus-like Syndrome
Some patients have developed symptoms that are like the symptoms of Lupus. If you develop any of the following symptoms, your doctor may decide to stop your treatment with AVSOLA.

- chest discomfort or pain that does not go away
- shortness of breath

- joint pain
- rash on the cheeks or arms that gets worse in the sun

Psoriasis
Some people receiving infliximab products had new psoriasis or worsening of psoriasis they already had. Tell your doctor if you develop red scaly patches or raised bumps on the skin that are filled with pus. Your doctor may decide to stop your treatment with AVSOLA.
The most common side effects of infliximab products include:

- respiratory infections, such as sinus infections and sore throat
- headache

- coughing
- stomach pain

Infusion reactions can happen up to 2 hours after your infusion of AVSOLA.
Symptoms of infusion reactions may include:

- fever
- chills
- chest pain
- low blood pressure or high blood pressure

- shortness of breath
- rash
- itching

Children with Crohn's disease who received infliximab showed some differences in side effects of treatment compared with adults with Crohn's disease. The side effects that happened more in children were: anemia (low red blood cells), leukopenia (low white blood cells), flushing (redness or blushing), viral infections, neutropenia (low neutrophils, the white blood cells that fight infection), bone fracture, bacterial infection and allergic reactions of the breathing tract. Among patients who received infliximab for ulcerative colitis in clinical studies, more children had infections as compared with adults.
Tell your doctor about any side effect that bothers you or does not go away.
These are not all of the side effects with AVSOLA. Ask your doctor or pharmacist for more information.
Call your doctor for medical advice about side effects. You may report side effects to FDA at 1-800-FDA-1088.

General information about AVSOLA
Medicines are sometimes prescribed for purposes other than those listed in a Medication Guide.
You can ask your doctor or pharmacist for information about AVSOLA that is written for health professionals.
For more information go to www.AVSOLA.com, or call 1- 800-77-AMGEN (1-800-772-6436).

What are the ingredients in AVSOLA?
The active ingredient is infliximab-axxq.
The inactive ingredients in AVSOLA include: dibasic sodium phosphate anhydrous, monobasic sodium phosphate monohydrate, polysorbate 80, and sucrose. No preservatives are present.
AVSOLA® (infliximab-axxq)
Manufactured by: Amgen, Inc. One Amgen Center Drive, Thousand Oaks, CA 91320-1799
U.S. License No. 1080
© 2021, 2025 Amgen, Inc. All rights reserved

This Medication Guide has been approved by the U.S. Food and Drug Administration

Revised: 8/2025

[part number] v3

PRINCIPAL DISPLAY PANEL - 100 mg Vial Carton Label

100
mg/vial

AMGEN®

NDC 55513-670-01

AVSOLA®
(infliximab-axxq)
For Injection

100 mg/vial

For Intravenous infusion only

Single-Dose Vial. Discard unused portion.

Contents: Each carton contains one 100 mg AVSOLA Single-Dose Vial.
ATTENTION: Dispense the enclosed Medication Guide to each patient
Reconstitute and Dilute before Intravenous Infusion. Infuse over at least 2 hours with an in-line filter.
Protect from light.
Dosage: See Prescribing Information.

Rx Only